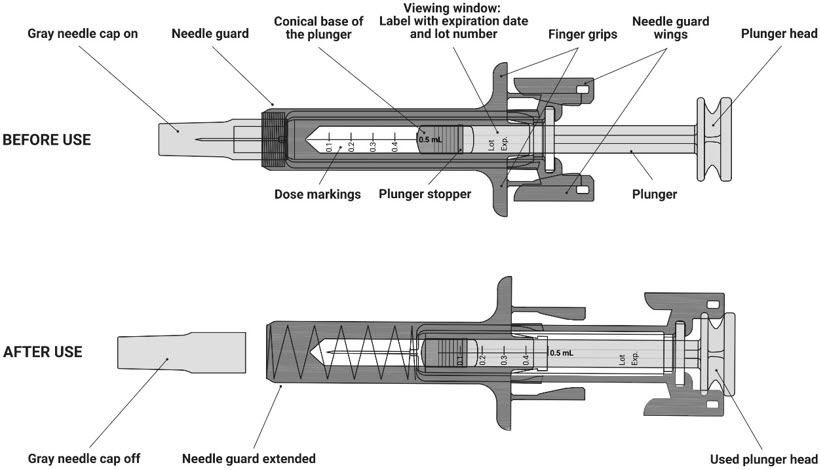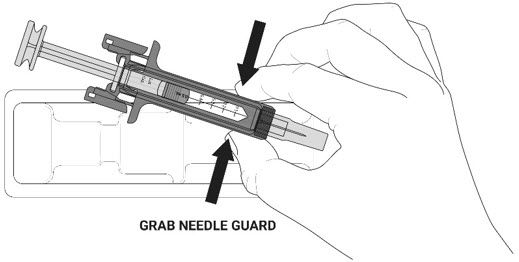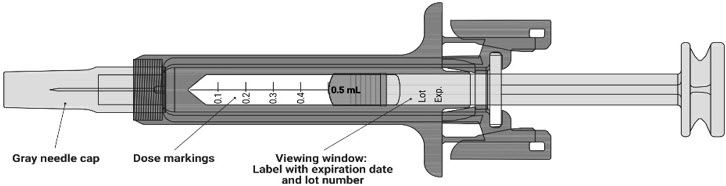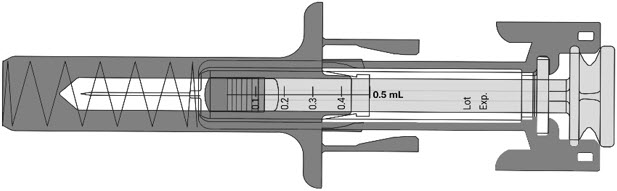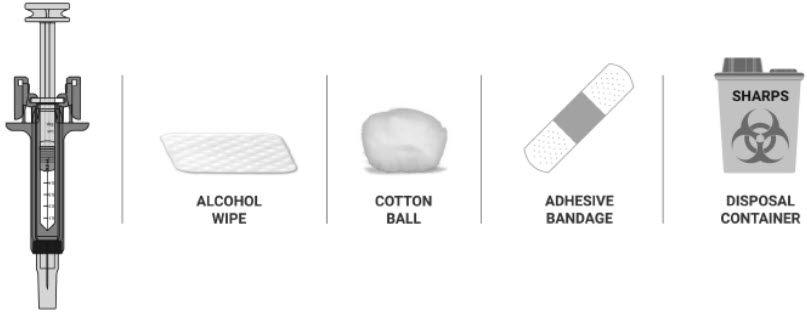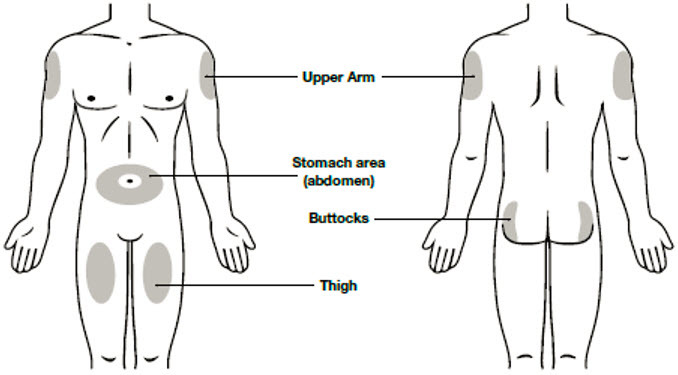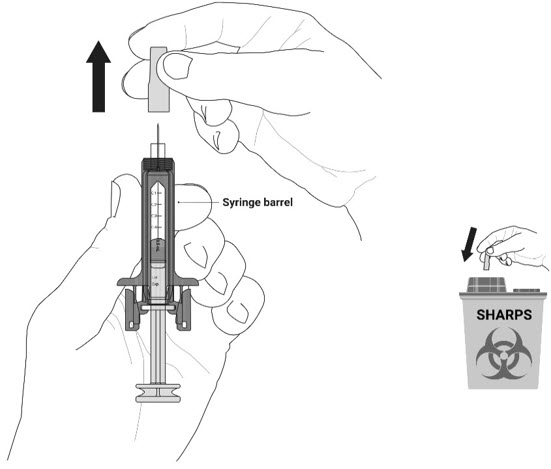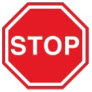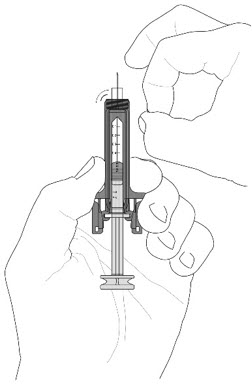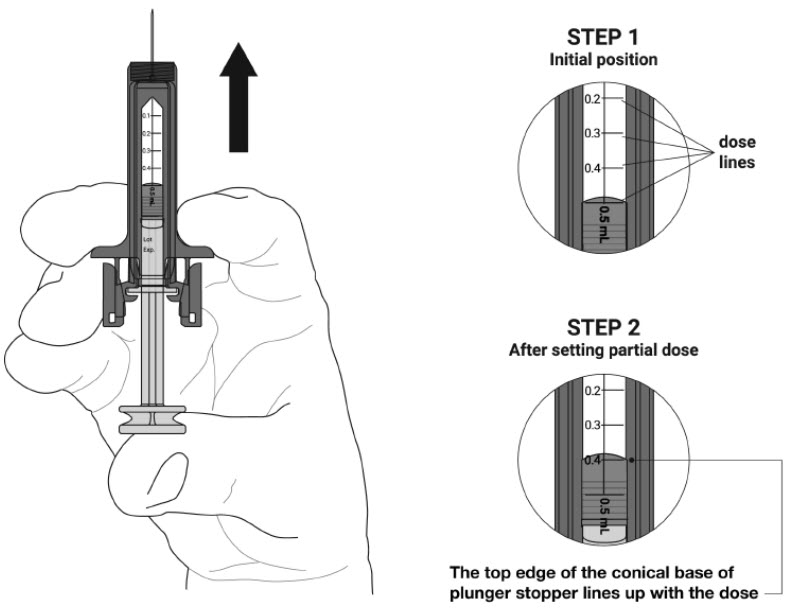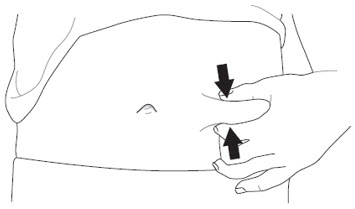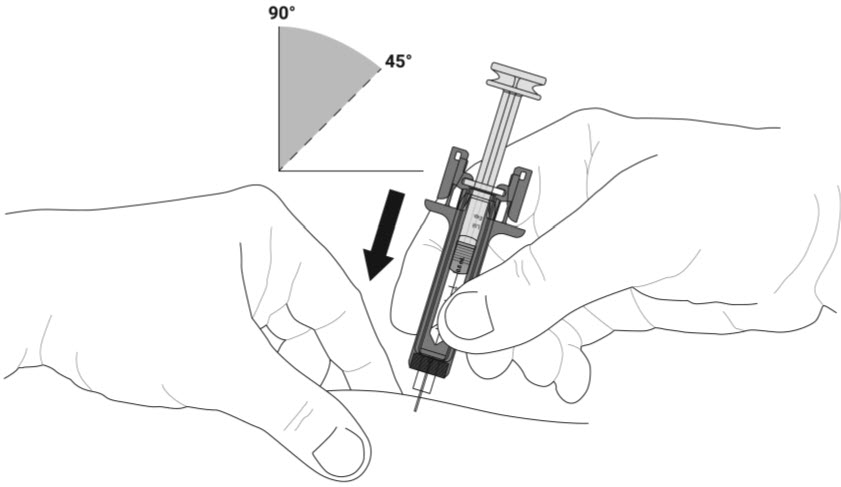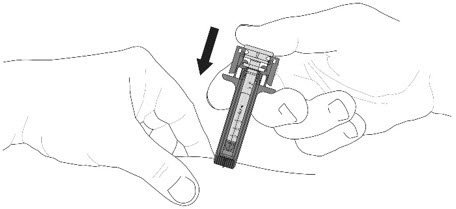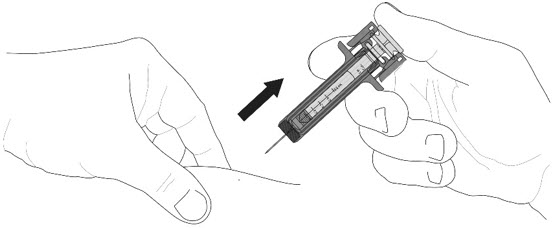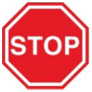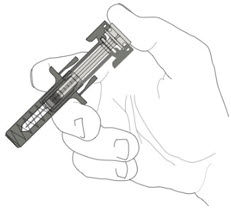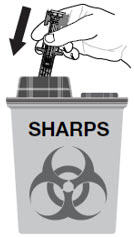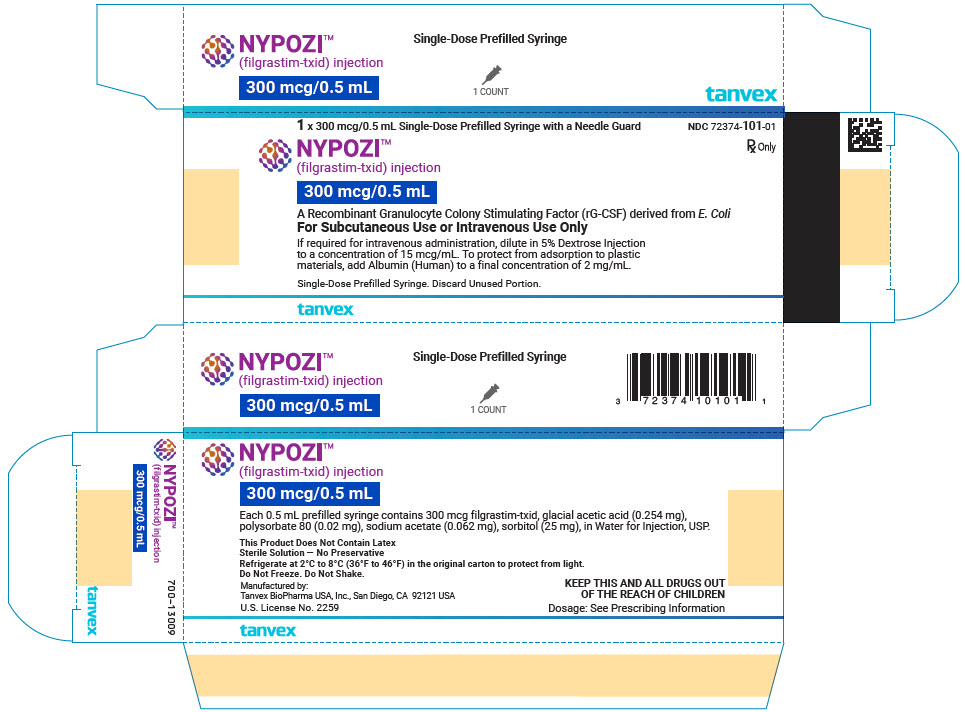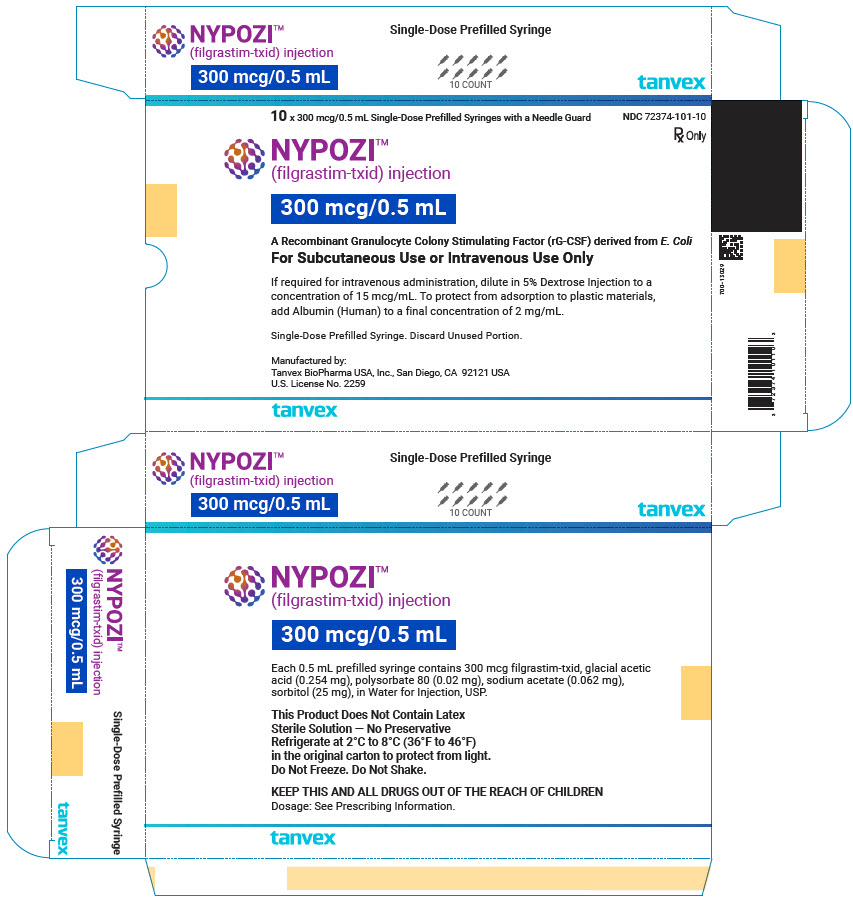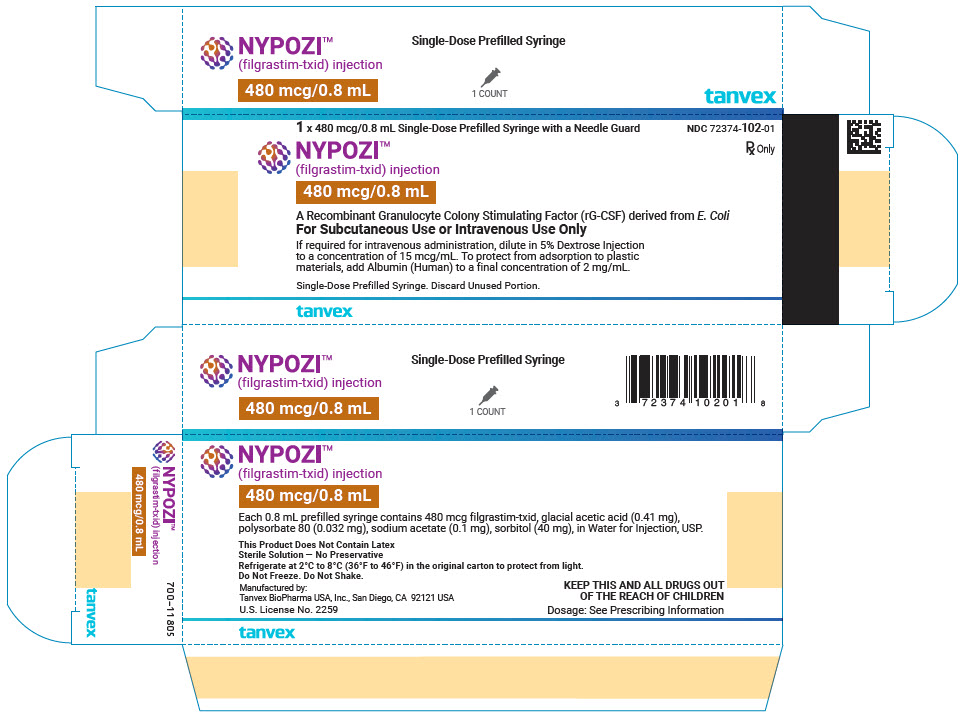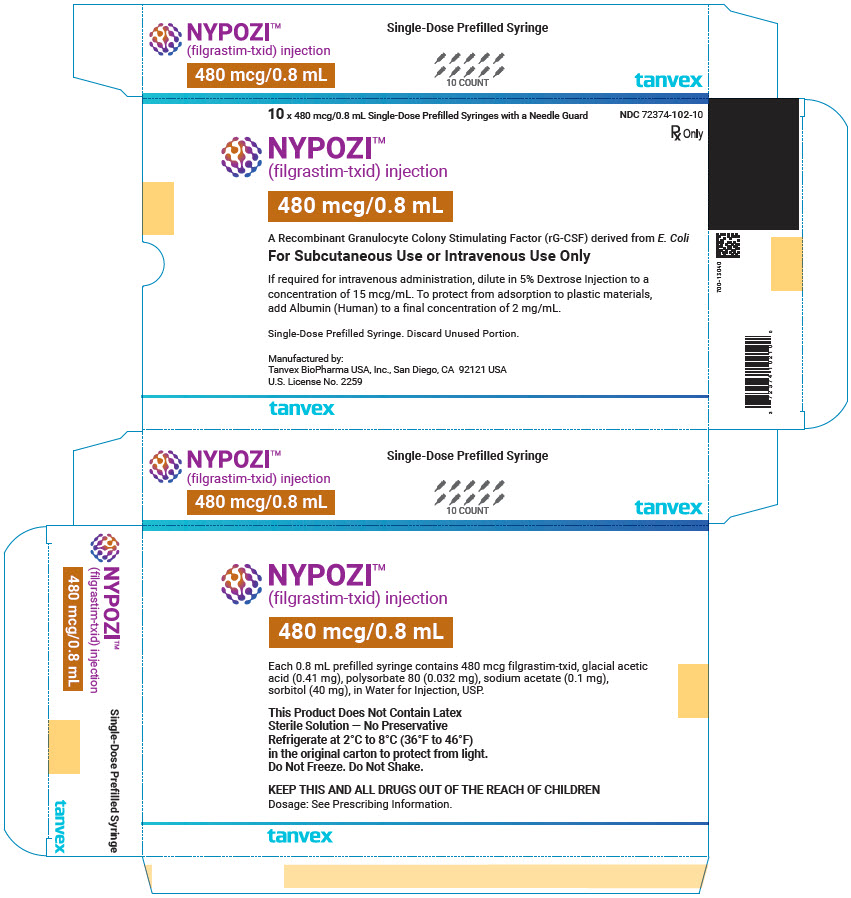 DRUG LABEL: NYPOZI
NDC: 72374-101 | Form: INJECTION
Manufacturer: Tanvex BioPharma USA, Inc.
Category: prescription | Type: HUMAN PRESCRIPTION DRUG LABEL
Date: 20260115

ACTIVE INGREDIENTS: FILGRASTIM 300 ug/300 ug

HIGHLIGHTS OF PRESCRIBING INFORMATION

These highlights do not include all the information needed to use NYPOZI safely and effectively. See full prescribing information for NYPOZI.
NYPOZI™ (filgrastim-txid) injection, for subcutaneous or intravenous use
Initial U.S. Approval: 2024
NYPOZI (filgrastim-txid) is biosimilar [Biosimilar means that the biological product is approved based on data demonstrating that it is highly similar to an FDA-approved biological product, known as a reference product, and that there are no clinically meaningful differences between the biosimilar product and the reference product. Biosimilarity of NYPOZI has been demonstrated for the condition(s) of use (e.g., indication(s), dosing regimen(s)), strength(s), dosage form(s), and route(s) of administration described in its Full Prescribing Information.] to NEUPOGEN® (filgrastim).

1 INDICATIONS AND USAGE

NYPOZI is a leukocyte growth factor indicated to:

- Decrease the incidence of infection, as manifested by febrile neutropenia, in patients with nonmyeloid malignancies receiving myelosuppressive anti-cancer drugs associated with a significant incidence of severe neutropenia with fever (1.1)
- Reduce the time to neutrophil recovery and the duration of fever, following induction or consolidation chemotherapy treatment of patients with acute myeloid leukemia (AML) (1.2)
- Reduce the duration of neutropenia and neutropenia-related clinical sequelae, e.g., febrile neutropenia, in patients with nonmyeloid malignancies undergoing myeloablative chemotherapy followed by bone marrow transplantation (BMT) (1.3)
- Mobilize autologous hematopoietic progenitor cells into the peripheral blood for collection by leukapheresis (1.4)
- Reduce the incidence and duration of sequelae of severe neutropenia (e.g.‚ fever‚ infections‚ oropharyngeal ulcers) in symptomatic patients with congenital neutropenia‚ cyclic neutropenia‚ or idiopathic neutropenia (1.5)
- Increase survival in patients acutely exposed to myelosuppressive doses of radiation (Hematopoietic Syndrome of Acute Radiation Syndrome) (1.6)

2 DOSAGE AND ADMINISTRATION

- Patients with cancer receiving myelosuppressive chemotherapy or induction and/or consolidation chemotherapy for AML
  - Recommended starting dose is 5 mcg/kg/day by subcutaneous injection, short intravenous infusion (15 to 30 minutes), or continuous intravenous infusion. See Full Prescribing Information for recommended dosage adjustments and timing of administration (2.1)
- Patients with cancer undergoing bone marrow transplantation:
  - 10 mcg/kg/day given as an intravenous infusion no longer than 24 hours. See Full Prescribing Information for recommended dosage adjustments and timing of administration (2.2)
- Patients undergoing autologous peripheral blood progenitor cell collection and therapy
  - 10 mcg/kg/day subcutaneous injection (2.3)
  - Administer for at least 4 days before first leukapheresis procedure and continue until last leukapheresis (2.3)
- Patients with congenital neutropenia
  - Recommended starting dose is 6 mcg/kg subcutaneous injection twice daily (2.4)
- Patients with cyclic or idiopathic neutropenia
  - Recommended starting dose is 5 mcg/kg subcutaneous injection daily (2.4)
- Patients acutely exposed to myelosuppressive doses of radiation
  - 10 mcg/kg/day subcutaneous injection (2.5)
- Direct administration of less than 0.3 mL (180 mcg) is not recommended due to potential for dosing errors (2.6)

3 DOSAGE FORMS AND STRENGTHS

- Injection: 300 mcg/0.5 mL in a single-dose prefilled syringe (3)
- Injection: 480 mcg/0.8 mL in a single-dose prefilled syringe (3)

4 CONTRAINDICATIONS

Patients with a history of serious allergic reactions to human granulocyte colony-stimulating factors such as filgrastim products or pegfilgrastim products (4)

5 WARNINGS AND PRECAUTIONS

- Fatal splenic rupture: Evaluate patients who report left upper abdominal or shoulder pain for an enlarged spleen or splenic rupture. (5.1)
- Acute respiratory distress syndrome (ARDS): Evaluate patients who develop fever and lung infiltrates or respiratory distress for ARDS. Discontinue NYPOZI in patients with ARDS. (5.2)
- Serious allergic reactions, including anaphylaxis: Permanently discontinue NYPOZI in patients with serious allergic reactions. (5.3)
- Fatal sickle cell crises: Discontinue NYPOZI if sickle cell crisis occurs. (5.4)
- Glomerulonephritis: Evaluate and consider dose-reduction or interruption of NYPOZI if causality is likely. (5.5)
- Myelodysplastic Syndrome (MDS) and Acute Myeloid Leukemia (AML): Monitor patients with breast and lung cancer using NYPOZI in conjunction with chemotherapy and/or radiotherapy for signs and symptoms of MDS/AML. (5.8)
- Thrombocytopenia: Monitor platelet counts. (5.9)

6 ADVERSE REACTIONS

Most common adverse reactions in patients:

- With nonmyeloid malignancies receiving myelosuppressive anti-cancer drugs (≥ 5% difference in incidence compared to placebo) are pyrexia, pain, rash, cough, and dyspnea. (6.1)
- With AML (≥ 2% difference in incidence) are pain, epistaxis and rash. (6.1)
- With nonmyeloid malignancies undergoing myeloablative chemotherapy followed by BMT (≥ 5% difference in incidence) is rash. (6.1)
- Undergoing peripheral blood progenitor cell mobilization and collection (≥ 5% incidence) are bone pain, pyrexia and headache. (6.1)
- With severe chronic neutropenia (SCN) (≥ 5% difference in incidence) are pain, anemia, epistaxis, diarrhea, hypoesthesia and alopecia. (6.1)

To report SUSPECTED ADVERSE REACTIONS, contact Tanvex BioPharma USA at 1-833-826-8398 or FDA at 1-800-FDA-1088 or www.fda.gov/medwatch.

FULL PRESCRIBING INFORMATION

1 INDICATIONS AND USAGE

1.1 Patients with Cancer Receiving Myelosuppressive Chemotherapy

NYPOZI is indicated to decrease the incidence of infection‚ as manifested by febrile neutropenia‚ in patients with nonmyeloid malignancies receiving myelosuppressive anti-cancer drugs associated with a significant incidence of severe neutropenia with fever [see Clinical Studies (14.1)].

1.2 Patients with Acute Myeloid Leukemia Receiving Induction or Consolidation Chemotherapy

NYPOZI is indicated for reducing the time to neutrophil recovery and the duration of fever, following induction or consolidation chemotherapy treatment of patients with acute myeloid leukemia (AML) [see Clinical Studies (14.2)].

1.3 Patients with Cancer Undergoing Bone Marrow Transplantation

NYPOZI is indicated to reduce the duration of neutropenia and neutropenia-related clinical sequelae‚ e.g.‚ febrile neutropenia, in patients with nonmyeloid malignancies undergoing myeloablative chemotherapy followed by bone marrow transplantation [see Clinical Studies (14.3)].

1.4 Patients Undergoing Autologous Peripheral Blood Progenitor Cell Collection and Therapy

NYPOZI is indicated for the mobilization of autologous hematopoietic progenitor cells into the peripheral blood for collection by leukapheresis [see Clinical Studies (14.4)].

1.5 Patients with Severe Chronic Neutropenia

NYPOZI is indicated for chronic administration to reduce the incidence and duration of sequelae of neutropenia (e.g.‚ fever‚ infections‚ oropharyngeal ulcers) in symptomatic patients with congenital neutropenia‚ cyclic neutropenia‚ or idiopathic neutropenia [see Clinical Studies (14.5)].

1.6 Patients Acutely Exposed to Myelosuppressive Doses of Radiation (Hematopoietic Syndrome of Acute Radiation Syndrome)

NYPOZI is indicated to increase survival in patients acutely exposed to myelosuppressive doses of radiation [see Clinical Studies (14.6)].

2 DOSAGE AND ADMINISTRATION

2.1 Dosage in Patients with Cancer Receiving Myelosuppressive Chemotherapy or Induction and/or Consolidation Chemotherapy for AML

The recommended starting dosage of NYPOZI is 5 mcg/kg/day‚ administered as a single daily injection by subcutaneous injection, by short intravenous infusion (15 to 30 minutes), or by continuous intravenous infusion. Obtain a complete blood count (CBC) and platelet count before instituting NYPOZI therapy and monitor twice weekly during therapy. Consider dose escalation in increments of 5 mcg/kg for each chemotherapy cycle‚ according to the duration and severity of the absolute neutrophil count (ANC) nadir. Recommend stopping NYPOZI if the ANC increases beyond 10‚000/mm^3 [see Warnings and Precautions (5.10)].

Administer NYPOZI at least 24 hours after cytotoxic chemotherapy. Do not administer NYPOZI within the 24-hour period prior to chemotherapy [see Warnings and Precautions (5.13)]. A transient increase in neutrophil count is typically seen 1 to 2 days after initiation of filgrastim therapy. Therefore, to ensure a sustained therapeutic response‚ administer NYPOZI daily for up to 2 weeks or until the ANC has reached 10‚000/mm^3 following the expected chemotherapy-induced neutrophil nadir. The duration of NYPOZI therapy needed to attenuate chemotherapy-induced neutropenia may be dependent on the myelosuppressive potential of the chemotherapy regimen employed.

2.2 Dosage in Patients with Cancer Undergoing Bone Marrow Transplantation

The recommended dosage of NYPOZI following bone marrow transplantation (BMT) is 10 mcg/kg/day given as an intravenous infusion no longer than 24 hours. Administer the first dose of NYPOZI at least 24 hours after cytotoxic chemotherapy and at least 24 hours after bone marrow infusion. Monitor CBCs and platelet counts frequently following marrow transplantation.

During the period of neutrophil recovery‚ titrate the daily dosage of NYPOZI against the neutrophil response (see Table 1).

Table 1. Recommended Dosage Adjustments During Neutrophil Recovery in Patients with Cancer Following BMT
Absolute Neutrophil Count | NYPOZI Dosage Adjustment
When ANC greater than 1,000/mm^3 for 3 consecutive days | Reduce to 5 mcg/kg/day [If ANC decreases to less than 1,000/mm^3 at any time during the 5 mcg/kg/day administration‚ increase NYPOZI to 10 mcg/kg/day‚ and then follow the above steps.]
Then, if ANC remains greater than 1,000/ mm^3 for 3 more consecutive days | Discontinue NYPOZI
Then, if ANC decreases to less than 1,000/mm^3 | Resume at 5 mcg/kg/day

2.3 Dosage in Patients Undergoing Autologous Peripheral Blood Progenitor Cell Collection and Therapy

The recommended dosage of NYPOZI for the mobilization of autologous peripheral blood progenitor cells (PBPC) is 10 mcg/kg/day given by subcutaneous injection. Administer NYPOZI for at least 4 days before the first leukapheresis procedure and continue until the last leukapheresis. Although the optimal duration of NYPOZI administration and leukapheresis schedule have not been established‚ administration of filgrastim for 6 to 7 days with leukaphereses on days 5‚ 6‚ and 7 was found to be safe and effective [see Clinical Studies (14.4)]. Monitor neutrophil counts after 4 days of NYPOZI and discontinue NYPOZI if the white blood cell (WBC) count rises to greater than 100‚000/mm^3.

2.4 Dosage in Patients with Severe Chronic Neutropenia

Prior to starting NYPOZI in patients with suspected chronic neutropenia, confirm the diagnosis of severe chronic neutropenia (SCN) by evaluating serial CBCs with differential and platelet counts‚ and evaluating bone marrow morphology and karyotype. The use of NYPOZI prior to confirmation of a correct diagnosis of SCN may impair diagnostic efforts and may thus impair or delay evaluation and treatment of an underlying condition‚ other than SCN‚ causing the neutropenia.

The recommended starting dosage in patients with Congenital Neutropenia is 6 mcg/kg as a twice daily subcutaneous injection and the recommended starting dosage in patients with Idiopathic or Cyclic Neutropenia is 5 mcg/kg as a single daily subcutaneous injection.

Dosage Adjustments in Patients with Severe Chronic Neutropenia

Chronic daily administration is required to maintain clinical benefit. Individualize the dosage based on the patient's clinical course as well as ANC. In the SCN postmarketing surveillance study, the reported median daily doses of filgrastim were: 6 mcg/kg (congenital neutropenia), 2.1 mcg/kg (cyclic neutropenia), and 1.2 mcg/kg (idiopathic neutropenia). In rare instances, patients with congenital neutropenia have required doses of filgrastim greater than or equal to 100 mcg/kg/day.

Monitor CBCs for Dosage Adjustments

During the initial 4 weeks of NYPOZI therapy and during the 2 weeks following any dosage adjustment‚ monitor CBCs with differential and platelet counts. Once a patient is clinically stable‚ monitor CBCs with differential and platelet counts monthly during the first year of treatment. Thereafter, if the patient is clinically stable, less frequent routine monitoring is recommended.

2.5 Dosage in Patients Acutely Exposed to Myelosuppressive Doses of Radiation (Hematopoietic Syndrome of Acute Radiation Syndrome)

The recommended dose of NYPOZI is 10 mcg/kg as a single daily subcutaneous injection for patients exposed to myelosuppressive doses of radiation. Administer NYPOZI as soon as possible after suspected or confirmed exposure to radiation doses greater than 2 gray (Gy).

Estimate a patient's absorbed radiation dose (i.e., level of radiation exposure) based on information from public health authorities, biodosimetry if available, or clinical findings such as time to onset of vomiting or lymphocyte depletion kinetics.

Obtain a baseline CBC and then serial CBCs approximately every third day until the ANC remains greater than 1,000/mm^3 for 3 consecutive CBCs. Do not delay administration of NYPOZI if a CBC is not readily available.

Continue administration of NYPOZI until the ANC remains greater than 1,000/mm^3 for 3 consecutive CBCs or exceeds 10,000/mm^3 after a radiation-induced nadir.

2.6 Important Administration Instructions

NYPOZI is supplied in single-dose prefilled syringes (for subcutaneous or intravenous use) [see Dosage Forms and Strengths (3)]. Prior to use‚ remove the prefilled syringe from the refrigerator and allow NYPOZI to reach room temperature for a minimum of 30 minutes and a maximum of 24 hours. Discard any prefilled syringe left at room temperature for greater than 24 hours. Parenteral drug products should be inspected visually for particulate matter and discoloration prior to administration, whenever solution and container permit. Do not administer NYPOZI if particulates or discoloration are observed.

Discard unused portion of NYPOZI in prefilled syringes. Do not save unused drug for later administration.

Subcutaneous Injection

Inject NYPOZI subcutaneously in the outer area of upper arms, abdomen, thighs, or upper outer areas of the buttock. If patients or caregivers are to administer NYPOZI, instruct them in appropriate injection technique and ask them to follow the subcutaneous injection procedures in the Instructions for Use for the prefilled syringe [see Patient Counseling Information (17)].

Training by a healthcare professional should aim to demonstrate to those patients and caregivers how to measure the dose using the prefilled syringe, and the focus should be on ensuring that a patient or caregiver can successfully perform all of the steps in the Instructions for Use for the NYPOZI prefilled syringe with BD UltraSafe Passive™ Needle Guard. If a patient or caregiver is not able to demonstrate that they can measure the dose and administer the product successfully, you should consider whether the patient is an appropriate candidate for self-administration of NYPOZI.

NYPOZI prefilled syringe with BD UltraSafe Passive™ Needle Guard is not designed to allow for direct administration of doses of less than 0.3 mL (180 mcg). The spring-mechanism of the needle guard apparatus affixed to the prefilled syringe interferes with the visibility of the graduation markings on the syringe barrel corresponding to 0.1 mL and 0.2 mL. The visibility of these markings is necessary to accurately measure doses of NYPOZI less than 0.3 mL (180 mcg) for direct administration to patients. Thus, the direct administration to patients requiring doses of less than 0.3 mL (180 mcg) is not recommended due to the potential for dosing errors.

Dilution

If required for intravenous administration, NYPOZI may be diluted in 5% Dextrose Injection to a concentration of 15 mcg/mL. NYPOZI diluted to 15 mcg/mL should be protected from adsorption to plastic materials by the addition of Albumin (Human) to a final concentration of 2 mg/mL. When diluted in 5% Dextrose plus Albumin (Human), NYPOZI is compatible with polyvinylchloride and polyolefin.

Do not dilute with Sodium Chloride Injection at any time, because the product may precipitate.

Diluted NYPOZI solution can be stored at room temperature for up to 14 hours. This 14 hour time period includes the time during room temperature storage of the infusion solution and the duration of the infusion.

If the patient or caregiver misses a dose of NYPOZI, instruct them to contact their healthcare provider.

3 DOSAGE FORMS AND STRENGTHS

NYPOZI is a clear, colorless to slightly yellowish, preservative-free solution available as:

Prefilled syringe:

- Injection: 300 mcg/0.5 mL in a single-dose prefilled syringe with BD UltraSafe Passive™ Needle Guard
- Injection: 480 mcg/0.8 mL in a single-dose prefilled syringe with BD UltraSafe Passive™ Needle Guard

4 CONTRAINDICATIONS

NYPOZI is contraindicated in patients with a history of serious allergic reactions to human granulocyte colony-stimulating factors such as filgrastim products or pegfilgrastim products [see Warnings and Precautions (5.3)].

5 WARNINGS AND PRECAUTIONS

5.1 Splenic Rupture

Splenic rupture, including fatal cases, has been reported following the administration of filgrastim products. Evaluate patients who report left upper abdominal or shoulder pain for an enlarged spleen or splenic rupture.

5.2 Acute Respiratory Distress Syndrome

Acute respiratory distress syndrome (ARDS) has been reported in patients receiving filgrastim products. Evaluate patients who develop fever and lung infiltrates or respiratory distress for ARDS. Discontinue NYPOZI in patients with ARDS.

5.3 Serious Allergic Reactions

Serious allergic reactions, including anaphylaxis, have been reported in patients receiving filgrastim products. The majority of reported events occurred upon initial exposure. Provide symptomatic treatment for allergic reactions. Allergic reactions, including anaphylaxis, in patients receiving filgrastim products can recur within days after the discontinuation of initial anti-allergic treatment. Permanently discontinue NYPOZI in patients with serious allergic reactions. NYPOZI is contraindicated in patients with a history of serious allergic reactions to human granulocyte colony-stimulating factors such as filgrastim products or pegfilgrastim products.

5.4 Sickle Cell Disorders

Severe and sometimes fatal sickle cell crises can occur, in patients with sickle cell disorders receiving filgrastim products. Discontinue NYPOZI if sickle cell crisis occurs.

5.5 Glomerulonephritis

Glomerulonephritis has occurred in patients receiving filgrastim products. The diagnoses were based upon azotemia, hematuria (microscopic and macroscopic), proteinuria, and renal biopsy. Generally, events of glomerulonephritis resolved after dose-reduction or discontinuation of filgrastim products. If glomerulonephritis is suspected, evaluate for cause. If causality is likely, consider dose-reduction or interruption of NYPOZI.

5.6 Alveolar Hemorrhage and Hemoptysis

Alveolar hemorrhage manifesting as pulmonary infiltrates and hemoptysis requiring hospitalization have been reported in healthy donors treated with filgrastim products undergoing peripheral blood progenitor cell (PBPC) collection mobilization. Hemoptysis resolved with discontinuation of filgrastim products. The use of NYPOZI for PBPC mobilization in healthy donors is not an approved indication.

5.7 Capillary Leak Syndrome

Capillary leak syndrome (CLS) has been reported after G-CSF administration, including filgrastim products, and is characterized by hypotension, hypoalbuminemia, edema, and hemoconcentration. Episodes vary in frequency, severity and may be life-threatening if treatment is delayed. Patients who develop symptoms of capillary leak syndrome should be closely monitored and receive standard symptomatic treatment, which may include a need for intensive care.

5.8 Myelodysplastic Syndrome (MDS) and Acute Myeloid Leukemia (AML)

Patients with Severe Chronic Neutropenia

Confirm the diagnosis of SCN before initiating NYPOZI therapy.

MDS and AML have been reported to occur in the natural history of congenital neutropenia without cytokine therapy. Cytogenetic abnormalities, transformation to MDS, and AML have also been observed in patients treated with filgrastim products for SCN. Based on available data including a postmarketing surveillance study, the risk of developing MDS and AML appears to be confined to the subset of patients with congenital neutropenia. Abnormal cytogenetics and MDS have been associated with the eventual development of myeloid leukemia. The effect of filgrastim products on the development of abnormal cytogenetics and the effect of continued filgrastim products administration in patients with abnormal cytogenetics or MDS are unknown. Monitor patients for signs and symptoms of MDS/AML in these settings. If a patient with SCN develops abnormal cytogenetics or myelodysplasia‚ the risks and benefits of continuing NYPOZI should be carefully considered.

Patients with Breast and Lung Cancer

MDS and AML have been associated with the use of filgrastim products in conjunction with chemotherapy and/or radiotherapy in patients with breast and lung cancer. Monitor patients for signs and symptoms of MDS/AML in these settings.

5.9 Thrombocytopenia

Thrombocytopenia has been reported in patients receiving filgrastim products. Monitor platelet counts.

5.10 Leukocytosis

Patients with Cancer Receiving Myelosuppressive Chemotherapy

White blood cell counts of 100‚000/mm^3 or greater were observed in approximately 2% of patients receiving filgrastim at dosages above 5 mcg/kg/day. In patients with cancer receiving NYPOZI as an adjunct to myelosuppressive chemotherapy‚ to avoid the potential risks of excessive leukocytosis‚ it is recommended that NYPOZI therapy be discontinued if the ANC surpasses 10‚000/mm^3 after the chemotherapy-induced ANC nadir has occurred. Monitor CBCs at least twice weekly during therapy. Dosages of NYPOZI that increase the ANC beyond 10‚000/mm^3 may not result in any additional clinical benefit. In patients with cancer receiving myelosuppressive chemotherapy‚ discontinuation of filgrastim therapy usually resulted in a 50% decrease in circulating neutrophils within 1 to 2 days‚ with a return to pretreatment levels in 1 to 7 days.

Peripheral Blood Progenitor Cell Collection and Therapy

During the period of administration of NYPOZI for PBPC mobilization in patients with cancer, discontinue NYPOZI if the leukocyte count rises to > 100,000/mm^3.

5.11 Cutaneous Vasculitis

Cutaneous vasculitis has been reported in patients treated with filgrastim products. In most cases‚ the severity of cutaneous vasculitis was moderate or severe. Most of the reports involved patients with SCN receiving long-term filgrastim therapy. Hold NYPOZI therapy in patients with cutaneous vasculitis. NYPOZI may be started at a reduced dose when the symptoms resolve and the ANC has decreased.

5.12 Potential Effect on Malignant Cells

NYPOZI is a growth factor that primarily stimulates neutrophils. The granulocyte-colony stimulating factor (G-CSF) receptor through which NYPOZI acts has also been found on tumor cell lines. The possibility that NYPOZI acts as a growth factor for any tumor type cannot be excluded. The safety of filgrastim products in chronic myeloid leukemia (CML) and myelodysplasia has not been established.

When NYPOZI is used to mobilize PBPC‚ tumor cells may be released from the marrow and subsequently collected in the leukapheresis product. The effect of reinfusion of tumor cells has not been well studied‚ and the limited data available are inconclusive.

5.13 Simultaneous Use with Chemotherapy and Radiation Therapy Not Recommended

The safety and efficacy of NYPOZI given simultaneously with cytotoxic chemotherapy have not been established. Because of the potential sensitivity of rapidly dividing myeloid cells to cytotoxic chemotherapy‚ do not use NYPOZI in the period 24 hours before through 24 hours after the administration of cytotoxic chemotherapy [see Dosage and Administration (2.2)].

The safety and efficacy of NYPOZI have not been evaluated in patients receiving concurrent radiation therapy. Avoid the simultaneous use of NYPOZI with chemotherapy and radiation therapy.

5.14 Nuclear Imaging

Increased hematopoietic activity of the bone marrow in response to growth factor therapy has been associated with transient positive bone-imaging changes. This should be considered when interpreting bone-imaging results.

5.15 Aortitis

Aortitis has been reported in patients receiving filgrastim products. It may occur as early as the first week after start of therapy. Manifestations may include generalized signs and symptoms such as fever, abdominal pain, malaise, back pain, and increased inflammatory markers (e.g., c-reactive protein and white blood cell count). Consider aortitis in patients who develop these signs and symptoms without known etiology. Discontinue NYPOZI if aortitis is suspected.

6 ADVERSE REACTIONS

The following serious adverse reactions are discussed in greater detail in other sections of the labeling:

- Splenic Rupture [see Warnings and Precautions (5.1)]
- Acute Respiratory Distress Syndrome [see Warnings and Precautions (5.2)]
- Serious Allergic Reactions [see Warnings and Precautions (5.3)]
- Sickle Cell Disorders [see Warnings and Precautions (5.4)]
- Glomerulonephritis [see Warnings and Precautions (5.5)]
- Alveolar Hemorrhage and Hemoptysis [see Warnings and Precautions (5.6)]
- Capillary Leak Syndrome [see Warnings and Precautions (5.7)]
- Myelodysplastic Syndrome [see Warnings and Precautions (5.8)]
- Acute Myeloid Leukemia [see Warnings and Precautions (5.8)]
- Thrombocytopenia [see Warnings and Precautions (5.9)]
- Leukocytosis [see Warnings and Precautions (5.10)]
- Cutaneous Vasculitis [see Warnings and Precautions (5.11)]
- Aortitis [see Warnings and Precautions (5.15)]

6.1 Clinical Trials Experience

Because clinical trials are conducted under widely varying conditions, adverse reaction rates observed in the clinical trials of a drug cannot be directly compared with rates in the clinical trials of another drug and may not reflect the rates observed in clinical practice.

Adverse Reactions in Patients with Cancer Receiving Myelosuppressive Chemotherapy

The following adverse reaction data in Table 2 are from three randomized, placebo-controlled studies in patients with:

- small cell lung cancer receiving standard dose chemotherapy with cyclophosphamide‚ doxorubicin‚ and etoposide (Study 1)
- small cell lung cancer receiving ifosfamide, doxorubicin‚ and etoposide (Study 2), and
- non-Hodgkin's lymphoma (NHL) receiving doxorubicin, cyclophosphamide, vindesine, bleomycin, methylprednisolone, and methotrexate ("ACVBP") or mitoxantrone, ifosfamide, mitoguazone, teniposide, methotrexate, folinic acid, methylprednisolone, and methotrexate ("VIM3") (Study 3).

A total of 451 patients were randomized to receive subcutaneous filgrastim 230 mcg/m^2 (Study 1), 240 mcg/m^2 (Study 2) or 4 or 5 mcg/kg/day (Study 3) (n = 294) or placebo (n = 157). The patients in these studies were median age 61 (range 29 to 78) years and 64% were male. The ethnicity was 95% Caucasian, 4% African American, and 1% Asian.

Table 2. Adverse Reactions in Patients with Cancer Receiving Myelosuppressive Chemotherapy (With ≥ 5% Higher Incidence in Filgrastim Compared to Placebo)
System Organ Class Preferred Term | Filgrastim (N = 294) | Placebo (N = 157)
Blood and lymphatic system disorders
Thrombocytopenia | 38% | 29%
Gastrointestinal disorders
Nausea | 43% | 32%
General disorders and administration site conditions
Pyrexia | 48% | 29%
Chest pain | 13% | 6%
Pain | 12% | 6%
Fatigue | 20% | 10%
Musculoskeletal and connective tissue disorders
Back pain | 15% | 8%
Arthralgia | 9% | 2%
Bone pain | 11% | 6%
Pain in extremity [Percent difference (Filgrastim – Placebo) was 4%.] | 7% | 3%
Nervous system disorders
Dizziness | 14% | 3%
Respiratory, thoracic and mediastinal disorders
Cough | 14% | 8%
Dyspnea | 13% | 8%
Skin and subcutaneous tissue disorders
Rash | 14% | 5%
Investigations
Blood lactate dehydrogenase increased | 6% | 1%
Blood alkaline phosphatase increased | 6% | 1%

Adverse events with ≥ 5% higher incidence in filgrastim patients compared to placebo and associated with the sequelae of the underlying malignancy or cytotoxic chemotherapy delivered included anemia, constipation, diarrhea, oral pain, vomiting, asthenia, malaise, edema peripheral, hemoglobin decreased, decreased appetite, oropharyngeal pain, and alopecia.

Adverse Reactions in Patients with Acute Myeloid Leukemia

Adverse reaction data below are from a randomized, double-blind, placebo-controlled study in patients with AML (Study 4) who received an induction chemotherapy regimen of intravenous daunorubicin days 1, 2, and 3; cytosine arabinoside days 1 to 7; and etoposide days 1 to 5 and up to 3 additional courses of therapy (induction 2, and consolidation 1, 2) of intravenous daunorubicin, cytosine arabinoside, and etoposide. The safety population included 518 patients randomized to receive either 5 mcg/kg/day filgrastim (n = 257) or placebo (n = 261). The median age was 54 (range 16 to 89) years and 54% were male.

Adverse reactions with ≥ 2% higher incidence in filgrastim patients compared to placebo included epistaxis, back pain, pain in extremity, erythema, and rash maculo-papular.

Adverse events with ≥ 2% higher incidence in filgrastim patients compared to placebo and associated with the sequelae of the underlying malignancy or cytotoxic chemotherapy included diarrhea, constipation, and transfusion reaction.

Adverse Reactions in Patients with Cancer Undergoing Bone Marrow Transplantation

The following adverse reaction data are from one randomized, no treatment-controlled study in patients with acute lymphoblastic leukemia or lymphoblastic lymphoma receiving high-dose chemotherapy (cyclophosphamide or cytarabine, and melphalan) and total body irradiation (Study 5) and one randomized, no treatment-controlled study in patients with Hodgkin's disease (HD) and NHL undergoing high-dose chemotherapy and autologous bone marrow transplantation (Study 6). Patients receiving autologous bone marrow transplantation only were included in the analysis. A total of 100 patients received either 30 mcg/kg/day as a 4-hour infusion (Study 5) or 10 mcg/kg/day or 30 mcg/kg/day as a 24-hour infusion (Study 6) filgrastim (n = 72), no treatment control or placebo (n = 28). The median age was 30 (range 15 to 57) years, 57% were male.

Adverse reactions with ≥ 5% higher incidence in filgrastim patients compared to patients receiving no filgrastim included rash and hypersensitivity.

Adverse reactions in patients receiving intensive chemotherapy followed by autologous BMT with ≥ 5% higher incidence in filgrastim patients compared to patients receiving no filgrastim included thrombocytopenia, anemia, hypertension, sepsis, bronchitis, and insomnia.

Adverse Reactions in Patients with Cancer Undergoing Autologous Peripheral Blood Progenitor Cell Collection

The adverse reaction data in Table 3 are from a series of 7 trials in patients with cancer undergoing mobilization of autologous peripheral blood progenitor cells for collection by leukapheresis. Patients (n = 166) in all these trials underwent a similar mobilization/collection regimen: filgrastim was administered for 6 to 8 days‚ in most cases the apheresis procedure occurred on days 5‚ 6, and 7. The dosage of filgrastim ranged between 5 to 30 mcg/kg/day and was administered subcutaneously by injection or continuous infusion. The median age was 39 (range 15 to 67) years, and 48% were male.

Table 3. Adverse Reactions in Patients with Cancer Undergoing Autologous PBPC in the Mobilization Phase (≥ 5% Incidence in Filgrastim Patients)
System Organ Class Preferred Term | Mobilization Phase (N = 166)
Musculoskeletal and connective tissue disorders
Bone pain | 30%
General disorders and administration site conditions
Pyrexia | 16%
Investigations
Blood alkaline phosphatase increased | 11%
Nervous system disorders
Headache | 10%

Adverse Reactions in Patients with Severe Chronic Neutropenia

The following adverse reaction data were identified in a randomized, controlled study in patients with SCN receiving filgrastim (Study 7). 123 patients were randomized to a 4-month observation period followed by subcutaneous filgrastim treatment or immediate subcutaneous filgrastim treatment. The median age was 12 years (range 7 months to 76 years) and 46% were male. The dosage of filgrastim was determined by the category of neutropenia. Initial dosage of filgrastim:

- Idiopathic neutropenia: 3.6 mcg/kg/day
- Cyclic neutropenia: 6 mcg/kg/day
- Congenital neutropenia: 6 mcg/kg/day divided 2 times per day

The dosage was increased incrementally to 12 mcg/kg/day divided 2 times per day if there was no response.

Adverse reactions with ≥ 5% higher incidence in filgrastim patients compared to patients receiving no filgrastim included arthralgia, bone pain, back pain, muscle spasms, musculoskeletal pain, pain in extremity, splenomegaly, anemia, upper respiratory tract infection, and urinary tract infection (upper respiratory tract infection and urinary tract infection were higher in the filgrastim arm, total infection related events were lower in filgrastim treated patients), epistaxis, chest pain, diarrhea, hypoesthesia, and alopecia.

6.2 Postmarketing Experience

The following adverse reactions have been identified during post-approval use of filgrastim products. Because these reactions are reported voluntarily from a population of uncertain size, it is not always possible to reliably estimate their frequency or establish a causal relationship to drug exposure.

- splenic rupture and splenomegaly (enlarged spleen) [see Warnings and Precautions (5.1)]
- acute respiratory distress syndrome [see Warnings and Precautions (5.2)]
- anaphylaxis [see Warnings and Precautions (5.3)]
- sickle cell disorders [see Warnings and Precautions (5.4)]
- glomerulonephritis [see Warnings and Precautions (5.5)]
- alveolar hemorrhage and hemoptysis [see Warnings and Precautions (5.6)]
- capillary leak syndrome [see Warnings and Precautions (5.7)]
- leukocytosis [see Warnings and Precautions (5.10)]
- cutaneous vasculitis [see Warnings and Precautions (5.11)]
- Sweet's syndrome (acute febrile neutrophilic dermatosis)
- decreased bone density and osteoporosis in pediatric patients receiving chronic treatment with filgrastim products
- myelodysplastic syndrome (MDS) and acute myeloid leukemia (AML) in patients with breast and lung cancer receiving chemotherapy and/or radiotherapy [see Warnings and Precautions (5.8)]
- aortitis [see Warnings and Precautions (5.15)]
- extramedullary hematopoiesis

8 USE IN SPECIFIC POPULATIONS

8.1 Pregnancy

Risk Summary

Available data from published studies, including several observational studies of pregnancy outcomes in women exposed to filgrastim products and those who were unexposed, have not established an association with filgrastim products use during pregnancy and major birth defects, miscarriage, or adverse maternal or fetal outcomes (see Data). Reports in the scientific literature have described transplacental passage of filgrastim in pregnant women when administered ≤ 30 hours prior to preterm delivery (≤ 30 weeks gestation). In animal reproduction studies, effects of filgrastim on prenatal development have been studied in rats and rabbits. No malformations were observed in either species. No maternal or fetal effects were observed in pregnant rats at doses up to 58 times the human doses. Filgrastim has been shown to have adverse effects in pregnant rabbits at doses 2 to 10 times higher than the human doses (see Data).

The estimated background risk of major birth defects and miscarriage for the indicated population is unknown. All pregnancies have a background risk of birth defect, loss, or other adverse outcomes. In the U.S. general population, the estimated background risks of major birth defects and miscarriage in clinically recognized pregnancies is 2-4% and 15- 20%, respectively.

Data

Human Data

Several observational studies based on the Severe Chronic Neutropenia International Registry (SCNIR) described pregnancy outcomes in women with severe chronic neutropenia (SCN) who were exposed to filgrastim products during pregnancy and women with SCN who were unexposed. No major differences were seen between treated and untreated women with respect to pregnancy outcome (including miscarriage and preterm labor), newborn complications (including birth weight), and infections. Methodological limitations of these studies include small sample size and lack of generalizability due to the underlying maternal condition.

Animal Data

Effects of filgrastim on prenatal development have been studied in rats and rabbits. No malformations were observed in either species. Filgrastim has been shown to have adverse effects in pregnant rabbits at doses 2 to 10 times higher than the human doses. In pregnant rabbits showing signs of maternal toxicity, reduced embryo-fetal survival (at 20 and 80 mcg/kg/day) and increased abortions (at 80 mcg/kg/day) were observed. In pregnant rats, no maternal or fetal effects were observed at doses up to 575 mcg/kg/day, which is approximately 58 times higher than the human dose of 10 mcg/kg/day.

Offspring of rats administered filgrastim during the peri-natal and lactation periods exhibited a delay in external differentiation and growth retardation (≥ 20 mcg/kg/day) and slightly reduced survival rate (100 mcg/kg/day).

8.2 Lactation

Risk Summary

There is published literature documenting transfer of filgrastim into human milk. There are a few case reports describing the use of filgrastim in breastfeeding mothers with no adverse effects noted in the infants. There are no data on the effects of filgrastim products on milk production. Other filgrastim products are secreted poorly into breast milk, and filgrastim products are not absorbed orally by neonates. The developmental and health benefits of breastfeeding should be considered along with the mother's clinical need for NYPOZI and any potential adverse effects on the breastfed child from NYPOZI or from the underlying maternal condition.

8.4 Pediatric Use

NYPOZI prefilled syringe with BD UltraSafe Passive™ Needle Guard may not accurately measure volumes less than 0.3 mL due to the needle spring mechanism design. Therefore, the direct administration of a volume less than 0.3 mL (180 mcg) is not recommended due to the potential for dosing errors.

In patients with cancer receiving myelosuppressive chemotherapy‚ 15 pediatric patients median age 2.6 (range 1.2 – 9.4) years with neuroblastoma were treated with myelosuppressive chemotherapy (cyclophosphamide‚ cisplatin‚ doxorubicin‚ and etoposide) followed by subcutaneous filgrastim at doses of 5, 10, or 15 mcg/kg/day for 10 days (n = 5/dose) (Study 8). The pharmacokinetics of filgrastim in pediatric patients after chemotherapy are similar to those in adults receiving the same weight-normalized doses, suggesting no age-related differences in the pharmacokinetics of filgrastim. In this population‚ filgrastim was well tolerated. There was one report of palpable splenomegaly and one report of hepatosplenomegaly associated with filgrastim therapy; however, the only consistently reported adverse event was musculoskeletal pain‚ which is no different from the experience in the adult population.

The safety and effectiveness of filgrastim have been established in pediatric patients with SCN [see Clinical Studies (14.5)]. In a phase 3 study (Study 7) to assess the safety and efficacy of filgrastim in the treatment of SCN, 123 patients with a median age of 12 years (range 7 months to 76 years) were studied. Of the 123 patients, 12 were infants (7 months to 2 years of age), 49 were children (2 to 12 years of age), and 9 were adolescents (12 to 16 years of age). Additional information is available from a SCN postmarketing surveillance study, which includes long-term follow-up of patients in the clinical studies and information from additional patients who entered directly into the postmarketing surveillance study. Of the 731 patients in the surveillance study, 429 were pediatric patients < 18 years of age (range 0.9 - 17) [see Indications and Usage (1.5), Dosage and Administration (2.5), and Clinical Studies (14.5)].

Long-term follow-up data from the postmarketing surveillance study suggest that height and weight are not adversely affected in patients who received up to 5 years of filgrastim treatment. Limited data from patients who were followed in the phase 3 study for 1.5 years did not suggest alterations in sexual maturation or endocrine function.

Pediatric patients with congenital types of neutropenia (Kostmann's syndrome, congenital agranulocytosis, or Schwachman-Diamond syndrome) have developed cytogenetic abnormalities and have undergone transformation to MDS and AML while receiving chronic filgrastim treatment. The relationship of these events to filgrastim products administration is unknown [see Warnings and Precautions (5.7), Adverse Reactions (6)].

The use of filgrastim to increase survival in pediatric patients acutely exposed to myelosuppressive doses of radiation is based on studies of filgrastim conducted in animals and clinical data supporting the use of filgrastim in other approved indications [see Dosage and Administration (2.1 to 2.4) and Clinical Studies (14.6)].

8.5 Geriatric Use

Among 855 subjects enrolled in 3 randomized, placebo-controlled trials of filgrastim treated-patients receiving myelosuppressive chemotherapy, there were 232 subjects age 65 or older, and 22 subjects age 75 or older. No overall differences in safety or effectiveness were observed between these subjects and younger subjects.

Clinical studies of filgrastim in other approved indications (i.e., BMT recipients, PBPC mobilization, and SCN) did not include sufficient numbers of subjects aged 65 and older to determine whether elderly subjects respond differently from younger subjects.

10 OVERDOSAGE

The maximum tolerated dose of filgrastim products has not been determined. In filgrastim clinical trials of patients with cancer receiving myelosuppressive chemotherapy‚ WBC counts > 100‚000/mm^3 have been reported in less than 5% of patients‚ but were not associated with any reported adverse clinical effects.

Patients in the BMT studies received up to 138 mcg/kg/day without toxic effects, although there was a flattening of the dose response curve above daily doses of greater than 10 mcg/kg/day.

11 DESCRIPTION

Filgrastim-txid, a leukocyte growth factor, is a 175 amino acid human granulocyte colony-stimulating factor (G-CSF) manufactured by recombinant DNA technology. Filgrastim-txid is produced by Escherichia coli (E. coli) bacteria into which has been inserted the human granulocyte colony-stimulating factor gene. Filgrastim-txid has a molecular weight of 18‚800 daltons. The protein has an amino acid sequence that is identical to the natural sequence predicted from human DNA sequence analysis‚ except for the addition of an N-terminal methionine necessary for expression in E. coli. Because filgrastim-txid is produced in E. coli‚ the product is non-glycosylated and thus differs from G-CSF isolated from a human cell.

NYPOZI (filgrastim-txid) injection is a sterile‚ clear‚ colorless to slightly yellowish‚ preservative-free liquid containing filgrastim-txid at a specific activity of 1.3 ± 0.3 × 10^8 IU/mg (as measured by a cell mitogenesis assay). The product is available in single-dose prefilled syringes for subcutaneous or intravenous use. The single-dose prefilled syringes contain either 300 mcg/0.5 mL or 480 mcg/0.8 mL of filgrastim-txid. The pH is 4.0. See table below for product composition of each single-dose prefilled syringe.

 | 300 mcg/0.5 mL Syringe | 480 mcg/0.8 mL Syringe
filgrastim-txid | 300 mcg | 480 mcg
glacial acetic acid | 0.254 mg | 0.41 mg
polysorbate 80 | 0.062 mg | 0.1 mg
sodium acetate | 0.02 mg | 0.032 mg
sorbitol | 25 mg | 40 mg
water for Injection USP q.s. ad [quantity sufficient to make] | 0.5 mL | 0.8 mL

12 CLINICAL PHARMACOLOGY

12.1 Mechanism of Action

Colony-stimulating factors are glycoproteins which act on hematopoietic cells by binding to specific cell surface receptors and stimulating proliferation‚ differentiation commitment‚ and some end-cell functional activation.

Endogenous G-CSF is a lineage-specific colony-stimulating factor that is produced by monocytes‚ fibroblasts, and endothelial cells. G-CSF regulates the production of neutrophils within the bone marrow and affects neutrophil progenitor proliferation‚ differentiation, and selected end-cell functions (including enhanced phagocytic ability‚ priming of the cellular metabolism associated with respiratory burst‚ antibody-dependent killing, and the increased expression of some cell surface antigens). G-CSF is not species-specific and has been shown to have minimal direct in vivo or in vitro effects on the production or activity of hematopoietic cell types other than the neutrophil lineage.

12.2 Pharmacodynamics

In phase 1 studies involving 96 patients with various nonmyeloid malignancies‚ administration of filgrastim resulted in a dose-dependent increase in circulating neutrophil counts over the dose range of 1 to 70 mcg/kg/day. This increase in neutrophil counts was observed whether filgrastim was administered intravenous (1 to 70 mcg/kg twice daily), subcutaneous (1 to 3 mcg/kg once daily)‚ or by continuous subcutaneous infusion (3 to 11 mcg/kg/day). With discontinuation of filgrastim therapy‚ neutrophil counts returned to baseline in most cases within 4 days. Isolated neutrophils displayed normal phagocytic (measured by zymosan-stimulated chemoluminescence) and chemotactic (measured by migration under agarose using N-formyl-methionyl-leucyl-phenylalanine [fMLP] as the chemotaxin) activity in vitro.

The absolute monocyte count was reported to increase in a dose-dependent manner in most patients receiving filgrastim; however, the percentage of monocytes in the differential count remained within the normal range. Absolute counts of both eosinophils and basophils did not change and were within the normal range following administration of filgrastim. Increases in lymphocyte counts following filgrastim administration have been reported in some normal subjects and patients with cancer.

White blood cell (WBC) differentials obtained during clinical trials have demonstrated a shift towards earlier granulocyte progenitor cells (left shift), including the appearance of promyelocytes and myeloblasts‚ usually during neutrophil recovery following the chemotherapy-induced nadir. In addition‚ Dohle bodies‚ increased granulocyte granulation‚ and hypersegmented neutrophils have been observed. Such changes were transient and were not associated with clinical sequelae, nor were they necessarily associated with infection.

12.3 Pharmacokinetics

Filgrastim products exhibit nonlinear pharmacokinetics. Clearance is dependent on filgrastim product concentration and neutrophil count: G-CSF receptor-mediated clearance is saturated by high concentration of filgrastim products and is diminished by neutropenia. In addition, filgrastim products are cleared by the kidney.

Subcutaneous administration of 3.45 mcg/kg and 11.5 mcg/kg of filgrastim resulted in maximum serum concentrations of 4 and 49 ng/mL‚ respectively‚ within 2 to 8 hours. After intravenous administration, the volume of distribution averaged 150 mL/kg and the elimination half-life was approximately 3.5 hours in both normal subjects and subjects with cancer. Clearance rate of filgrastim was approximately 0.5 to 0.7 mL/minute/kg. Single parenteral doses or daily intravenous doses‚ over a 14-day period‚ resulted in comparable half-lives. The half-lives were similar for intravenous administration (231 minutes‚ following doses of 34.5 mcg/kg) and for subcutaneous administration (210 minutes‚ following filgrastim dosages of 3.45 mcg/kg). Continuous 24 hour intravenous infusions of 20 mcg/kg over an 11 to 20 day period produced steady state serum concentrations of filgrastim with no evidence of drug accumulation over the time period investigated. The absolute bioavailability of filgrastim after subcutaneous administration is 60% to 70%.

Specific Populations

Patients Acutely Exposed to Myelosuppressive Doses of Radiation

The pharmacokinetics of filgrastim products is not available in patients acutely exposed to myelosuppressive doses of radiation. Based on limited pharmacokinetics data in irradiated non-human primates, the area under the time-concentration curve (AUC), reflecting the exposure to filgrastim in non-human primates at 10 mcg/kg dose of filgrastim, appears to be similar to that in humans at 5 mcg/kg. Simulations conducted using the population pharmacokinetic model indicates that the exposures to filgrastim at a filgrastim dose of 10 mcg/kg in patients acutely exposed to myelosuppressive doses of radiation are expected to exceed the exposures at a dose of 10 mcg/kg in irradiated non-human primates.

Pediatric Patients: The pharmacokinetics of filgrastim in pediatric patients after chemotherapy are similar to those in adult patients receiving the same weight-normalized doses, suggesting no age-related differences in the pharmacokinetics of filgrastim products [see Use in Specific Populations (8.4)].

Renal Impairment: In a study with healthy volunteers, subjects with moderate renal impairment, and subjects with end stage renal disease (n=4 per group), higher serum concentrations were observed in subjects with end-stage renal disease. However, dose adjustment in patients with renal impairment is not necessary.

Hepatic Impairment: Pharmacokinetics and pharmacodynamics of filgrastim are similar between subjects with hepatic impairment and healthy subjects (n = 12/group). The study included 10 subjects with mild hepatic impairment (Child-Pugh Class A) and 2 subjects with moderate hepatic impairment (Child-Pugh Class B). Therefore, NYPOZI dose adjustment in patients with hepatic impairment is not necessary.

12.6 Immunogenicity

The observed incidence of anti-drug antibodies is highly dependent on the sensitivity and specificity of the assay. Differences in assay methods preclude meaningful comparisons of the incidence of anti-drug antibodies in the studies described below with the incidence of anti-drug antibodies in other studies, including those of filgrastim or of other filgrastim products.

While available data suggest that a small proportion of patients developed binding antibodies to filgrastim products, the nature and specificity of these antibodies has not been adequately studied. In clinical studies using filgrastim, the incidence of antibodies binding to filgrastim was 3% (11/333). In these 11 patients, no evidence of a neutralizing response was observed using a cell based bioassay. Because of the low occurrence of anti-drug antibodies, the effect of these antibodies on the pharmacokinetics, pharmacodynamics, safety, and/or effectiveness of filgrastim products is unknown.

Cytopenias resulting from an antibody response to exogenous growth factors have been reported on rare occasions in patients treated with other recombinant growth factors.

13 NONCLINICAL TOXICOLOGY

13.1 Carcinogenesis, Mutagenesis, Impairment of Fertility

The carcinogenic potential of filgrastim products has not been studied. Filgrastim failed to induce bacterial gene mutations in either the presence or absence of a drug metabolizing enzyme system. Filgrastim had no observed effect on the fertility of male or female rats at doses up to 500 mcg/kg.

13.2 Animal Toxicology and/or Pharmacology

Filgrastim was administered to monkeys‚ dogs‚ hamsters‚ rats‚ and mice as part of a nonclinical toxicology program, which included studies up to 1-year duration.

In the repeated-dose studies‚ changes observed were attributable to the expected pharmacological actions of filgrastim (i.e.‚ dose-dependent increases in white blood cell counts‚ increased circulating segmented neutrophils‚ and increased myeloid:erythroid ratio in bone marrow). Histopathologic examination of the liver and spleen revealed evidence of ongoing extramedullary granulopoiesis, and dose-related increases in spleen weight were seen in all species. These changes all reversed after discontinuation of treatment.

14 CLINICAL STUDIES

14.1 Patients with Cancer Receiving Myelosuppressive Chemotherapy

The safety and efficacy of filgrastim to decrease the incidence of infection‚ as manifested by febrile neutropenia‚ in patients with nonmyeloid malignancies receiving myelosuppressive anti-cancer drugs were established in a randomized‚ double-blind‚ placebo-controlled trial conducted in patients with small cell lung cancer (Study 1).

In Study 1, patients received up to 6 cycles of intravenous chemotherapy including intravenous cyclophosphamide and doxorubicin on day 1; and etoposide on days 1, 2, and 3 of 21-day cycles. Patients were randomized to receive filgrastim (n=99) at a dose of 230 mcg/m^2 (4 to 8 mcg/kg/day) or placebo (n=111). Study drug was administered subcutaneously daily beginning on day 4, for a maximum of 14 days. A total of 210 patients were evaluable for efficacy and 207 were evaluable for safety. The demographic and disease characteristics were balanced between arms with a median age of 62 (range 31 to 80) years; 64% males; 89% Caucasian; 72% extensive disease, and 28% limited disease.

The main efficacy endpoint was the incidence of febrile neutropenia. Febrile neutropenia was defined as an ANC < 1000/mm^3 and temperature > 38.2°C. Treatment with filgrastim resulted in a clinically and statistically significant reduction in the incidence of infection‚ as manifested by febrile neutropenia, 40% for filgrastim-treated patients and 76% for placebo-treated patients (p < 0.001). There were also statistically significant reductions in the incidence and overall duration of infection manifested by febrile neutropenia; the incidence, severity and duration of severe neutropenia (ANC < 500/mm^3); the incidence and overall duration of hospital admissions; and the number of reported days of antibiotic use.

14.2 Patients with Acute Myeloid Leukemia Receiving Induction or Consolidation Chemotherapy

The safety and efficacy of filgrastim to reduce the time to neutrophil recovery and the duration of fever, following induction or consolidation chemotherapy treatment of patients with acute myeloid leukemia (AML) was established in a randomized, double-blind‚ placebo-controlled‚ multi-center trial in patients with newly diagnosed, de novo AML (Study 4).

In Study 4 the initial induction therapy consisted of intravenous daunorubicin days 1, 2, and 3; cytosine arabinoside days 1 to 7; and etoposide days 1 to 5. Patients were randomized to receive subcutaneous filgrastim (n=259) at a dose of 5 mcg/kg/day or placebo (n=262) from 24 hours after the last dose of chemotherapy until neutrophil recovery (ANC ≥1000/mm^3 for 3 consecutive days or ≥ 10,000/mm^3 for 1 day) or for a maximum of 35 days. The demographic and disease characteristics were balanced between arms with a median age of 54 (range 16 to 89) years; 54% males; initial white blood cell count (65% - <25,000 /mm^3 and 27% > 100,000/mm^3); 29% unfavorable cytogenetics.

The main efficacy endpoint was median duration of severe neutropenia defined as neutrophil count < 500/mm^3. Treatment with filgrastim resulted in a clinically and statistically significant reduction in median number of days of severe neutropenia, filgrastim-treated patients 14 days, placebo-treated patients 19 days (p = 0.0001: difference of 5 days (95% CI: -6.0, -4.0)). There was a reduction in the median duration of intravenous antibiotic use, filgrastim-treated patients: 15 days versus placebo-treated patients: 18.5 days; a reduction in the median duration of hospitalization, filgrastim-treated patients: 20 days versus placebo-treated patients: 25 days.

There were no statistically significant differences between the filgrastim and the placebo groups in complete remission rate (69% - filgrastim, 68% - placebo), median time to progression of all randomized patients (165 days - filgrastim, 186 days - placebo), or median overall survival (380 days - filgrastim, 425 days - placebo).

14.3 Patients with Cancer Undergoing Bone Marrow Transplantation

The safety and efficacy of filgrastim to reduce the duration of neutropenia in patients with nonmyeloid malignancies undergoing myeloablative chemotherapy followed by autologous bone marrow transplantation was evaluated in 2 randomized controlled trials of patients with lymphoma (Study 6 and Study 9). The safety and efficacy of filgrastim to reduce the duration of neutropenia in patients undergoing myeloablative chemotherapy followed by allogeneic bone marrow transplantation was evaluated in a randomized placebo-controlled trial (Study10).

In Study 6 patients with Hodgkin's disease received a preparative regimen of intravenous cyclophosphamide, etoposide, and BCNU ("CVP"), and patients with non-Hodgkin's lymphoma received intravenous BCNU, etoposide, cytosine arabinoside and melphalan ("BEAM"). There were 54 patients randomized 1:1:1 to control, filgrastim 10 mcg/kg/day, and filgrastim 30 mcg/kg/day as a 24-hour continuous infusion starting 24 hours after bone marrow infusion for a maximum of 28 days. The median age was 33 (range 17 to 57) years; 56% males; 69% Hodgkin's disease and 31% non-Hodgkin's lymphoma.

The main efficacy endpoint was duration of severe neutropenia ANC < 500/mm^3. A statistically significant reduction in the median number of days of severe neutropenia (ANC < 500/mm^3) occurred in the filgrastim-treated groups versus the control group (23 days in the control group‚ 11 days in the 10 mcg/kg/day group‚ and 14 days in the 30 mcg/kg/day group [11 days in the combined treatment groups‚ p = 0.004]).

In Study 9, patients with Hodgkin's disease and non-Hodgkin's lymphoma received a preparative regimen intravenous cyclophosphamide, etoposide, and BCNU ("CVP"). There were 43 evaluable patients randomized to continuous subcutaneous infusion filgrastim 10 mcg/kg/day (n=19), filgrastim 30 mcg/kg/day (n=10) and no treatment (n=14) starting the day after marrow infusion for maximum of 28 days. The median age was 33 (range 17 to 56) years; 67% males; 28% Hodgkin's disease and 72% non-Hodgkin's lymphoma.

The main efficacy endpoint was duration of severe neutropenia. There was statistically significant reduction in the median number of days of severe neutropenia (ANC < 500/mm^3) in the filgrastim-treated groups versus the control group (21.5 days in the control group versus 10 days in the filgrastim-treated groups, p < 0.001). The number of days of febrile neutropenia was also reduced significantly in this study (13.5 days in the control group versus 5 days in the filgrastim-treated groups‚ p < 0.0001).

In Study 10, 70 patients scheduled to undergo bone marrow transplantation for multiple underlying conditions using multiple preparative regimens were randomized to receive filgrastim 300 mcg/m^2/day (n=33) or placebo (n=37) days 5 through 28 after marrow infusion. The median age was 18 (range 1 to 45) years, 56% males. The underlying disease was: 67% hematologic malignancy, 24% aplastic anemia, 9% other. A statistically significant reduction in the median number of days of severe neutropenia occurred in the treated group versus the control group (19 days in the control group and 15 days in the treatment group‚ p < 0.001) and time to recovery of ANC to ≥ 500/mm^3 (21 days in the control group and 16 days in the treatment group‚ p < 0.001).

14.4 Patients Undergoing Autologous Peripheral Blood Progenitor Cell Collection and Therapy

The safety and efficacy of filgrastim to mobilize autologous peripheral blood progenitor cells for collection by leukapheresis was supported by the experience in uncontrolled trials, and a randomized trial comparing hematopoietic stem cell rescue using filgrastim mobilized autologous peripheral blood progenitor cells to autologous bone marrow (Study 11). Patients in all these trials underwent a similar mobilization/collection regimen: filgrastim was administered for 6 to 7 days‚ in most cases the apheresis procedure occurred on days 5‚ 6, and 7. The dose of filgrastim ranged between 10 to 24 mcg/kg/day and was administered subcutaneously by injection or continuous intravenous infusion.

Engraftment was evaluated in 64 patients who underwent transplantation using filgrastim mobilized autologous hematopoietic progenitor cells in uncontrolled trials. Two of the 64 patients (3%) did not achieve the criteria for engraftment as defined by a platelet count ≥ 20‚000/mm^3 by day 28. In clinical trials of filgrastim for the mobilization of hematopoietic progenitor cells‚ filgrastim was administered to patients at doses between 5 to 24 mcg/kg/day after reinfusion of the collected cells until a sustainable ANC (≥ 500/mm^3) was reached. The rate of engraftment of these cells in the absence of filgrastim post transplantation has not been studied.

Study 11 was a randomized, unblinded study of patients with Hodgkin's disease or non-Hodgkin's lymphoma undergoing myeloablative chemotherapy‚ 27 patients received filgrastim-mobilized autologous hematopoietic progenitor cells and 31 patients received autologous bone marrow. The preparative regimen was intravenous BCNU, etoposide, cytosine arabinoside and melphalan ("BEAM"). Patients received daily filgrastim 24 hours after stem cell infusion at a dose of 5 mcg/kg/day. The median age was 33 (range 1 to 59) years; 64% males; 57% Hodgkin's disease and 43% non-Hodgkin's lymphoma. The main efficacy endpoint was number of days of platelet transfusions. Patients randomized to filgrastim-mobilized autologous peripheral blood progenitor cells compared to autologous bone marrow had significantly fewer days of platelet transfusions (median 6 vs 10 days).

14.5 Patients with Severe Chronic Neutropenia

The safety and efficacy of filgrastim to reduce the incidence and duration of sequelae of neutropenia (that is fever‚ infections, oropharyngeal ulcers) in symptomatic adult and pediatric patients with congenital neutropenia‚ cyclic neutropenia‚ or idiopathic neutropenia was established in a randomized controlled trial conducted in patients with severe neutropenia (Study 7).

Patients eligible for Study 7 had a history of severe chronic neutropenia documented with an ANC < 500/mm^3 on three occasions during a 6-month period, or in patients with cyclic neutropenia 5 consecutive days of ANC < 500/mm^3 per cycle. In addition, patients must have experienced a clinically significant infection during the previous 12 months. Patients were randomized to a 4-month observation period followed by filgrastim treatment or immediate filgrastim treatment. The median age was 12 years (range 7 months to 76 years); 46% males; 34% idiopathic, 17% cyclic, and 49% congenital neutropenia.

Filgrastim was administered subcutaneously. The dose of filgrastim was determined by the category of neutropenia.

Initial dose of filgrastim:

- Idiopathic neutropenia: 3.6 mcg/kg/day
- Cyclic neutropenia: 6 mcg/kg/day
- Congenital neutropenia: 6 mcg/kg/day divided 2 times per day

The dose was increased incrementally to 12 mcg/kg/day divided 2 times per day if there was no response.

The main efficacy endpoint was response to filgrastim treatment. ANC response from baseline (< 500/mm^3) was defined as follows:

- Complete response: median ANC > 1500/mm^3
- Partial response: median ANC ≥ 500/mm^3 and ≤ 1500/mm^3 with a minimum increase of 100%
- No response: median ANC < 500/mm^3

There were 112 of 123 patients who demonstrated a complete or partial response to filgrastim treatment.

Additional efficacy endpoints included a comparison between patients randomized to 4 months of observation and patients receiving filgrastim of the following parameters:

- incidence of infection
- incidence of fever
- duration of fever
- incidence, duration, and severity of oropharyngeal ulcers
- number of days of antibiotic use

The incidence for each of these 5 clinical parameters was lower in the filgrastim arm compared to the control arm for cohorts in each of the 3 major diagnostic categories. An analysis of variance showed no significant interaction between treatment and diagnosis‚ suggesting that efficacy did not differ substantially in the different diseases. Although filgrastim substantially reduced neutropenia in all patient groups‚ in patients with cyclic neutropenia‚ cycling persisted but the period of neutropenia was shortened to 1 day.

14.6 Patients Acutely Exposed to Myelosuppressive Doses of Radiation (Hematopoietic Syndrome of Acute Radiation Syndrome)

Efficacy studies of filgrastim products could not be conducted in humans with acute radiation syndrome for ethical and feasibility reasons. Approval of this indication was based on efficacy studies conducted in animals and data supporting the use of filgrastim for other approved indications [see Dosage and Administration (2.1 to 2.4)].

Because of the uncertainty associated with extrapolating animal efficacy data to humans, the selection of human dose for NYPOZI is aimed at providing exposures to filgrastim that exceed those observed in animal efficacy studies. The 10 mcg/kg daily dose is selected for humans exposed to myelosuppressive doses of radiation because the exposure associated with such a dose is expected to exceed the exposure associated with a 10 mcg/kg dose in non-human primates [see Clinical Pharmacology (12.3)]. The safety of filgrastim at a daily dose of 10 mcg/kg has been assessed on the basis of clinical experience in approved indications.

The efficacy of filgrastim was studied in a randomized, blinded, placebo-controlled study in a non-human primate model of radiation injury. The planned sample size was 62 animals, but the study was stopped at the interim analysis with 46 animals because efficacy was established. Rhesus macaques were randomized to a control (n = 22) or treated (n = 24) group. Animals were exposed to total body irradiation of 7.4 ± 0.15 Gy delivered at 0.8 ± 0.03 Gy/min, representing a dose that would be lethal in 50% of animals by 60 days of follow-up (LD50/60). Starting on day 1 after irradiation, animals received daily subcutaneous injections of placebo (5% dextrose in water) or filgrastim (10 mcg/kg/day). Blinded treatment was stopped when one of the following criteria was met: ANC ≥ 1,000/mm^3 for 3 consecutive days, or ANC ≥ 10,000/mm^3 for more than 2 consecutive days within study day 1 to 5, or ANC ≥ 10,000/mm^3 any time after study day 5. Animals received medical management consisting of intravenous fluids, antibiotics, blood transfusions, and other support as required.

Filgrastim significantly (at 0.023 level of significance) reduced 60-day mortality in the irradiated non-human primates: 21% mortality (5/24) in the filgrastim group compared to 59% mortality (13/22) in the control group.

16 HOW SUPPLIED/STORAGE AND HANDLING

NYPOZI (filgrastim-txid) injection is a clear, colorless to slightly yellowish, preservative-free solution supplied as prefilled syringes:

Single-dose‚ preservative-free, prefilled syringes with 29 gauge, half inch needle with a BD UltraSafe Passive™ Needle Guard, containing 300 mcg/0.5 mL of filgrastim-txid.

- Carton of 1 prefilled syringe (NDC 72374-101-01)
- Carton of 10 prefilled syringes (NDC 72374-101-10)

Single-dose‚ preservative-free, prefilled syringes with 29 gauge, half inch needle with a BD UltraSafe Passive™ Needle Guard, containing 480 mcg/0.8 mL of filgrastim-txid.

- Carton of 1 prefilled syringe (NDC 72374-102-01)
- Carton of 10 prefilled syringes (NDC 72374-102-10)

Storage:

Store NYPOZI in the refrigerator at 2°C to 8°C (36°F to 46°F) in the original carton to protect from light. Do not leave NYPOZI in direct sunlight. Avoid shaking. Do not freeze. Transport via pneumatic tube has not been studied. Prior to injection‚ NYPOZI may be allowed to reach room temperature for a maximum of 24 hours.

17 PATIENT COUNSELING INFORMATION

Advise the patient to read the FDA-approved patient labeling (Patient Information and Instructions for Use). Review the steps for direct patient administration with patients and caregivers. Training by the healthcare provider should aim to ensure that patients and caregivers can successfully perform all of the steps in the Instructions for Use of NYPOZI prefilled syringe with BD UltraSafe Passive™ Needle Guard, including showing the patient or caregiver how to measure the required dose, particularly if a patient is on a dose other than the entire prefilled syringe. If a patient or caregiver is not able to demonstrate that they can measure the dose and administer the product successfully, you should consider whether the patient is an appropriate candidate for self-administration of NYPOZI.

Advise patients of the following risks and potential risks with NYPOZI:

- Rupture or enlargement of the spleen may occur. Symptoms include left upper quadrant abdominal pain or left shoulder pain. Advise patients to report pain in these areas to their physician immediately [see Warnings and Precautions (5.1)].
- Dyspnea, with or without fever, progressing to Acute Respiratory Distress Syndrome, may occur. Advise patients to report dyspnea to their physician immediately [see Warnings and Precautions (5.2)].
- Serious allergic reactions may occur, which may be signaled by rash‚ facial edema‚ wheezing‚ dyspnea‚ hypotension‚ or tachycardia. Advise patient to seek immediate medical attention if signs or symptoms of hypersensitivity reaction occur [see Warnings and Precautions (5.3)].
- In patients with sickle cell disease, sickle cell crisis and death have occurred. Discuss potential risks and benefits for patients with sickle cell disease prior to the administration of human granulocyte colony-stimulating factors [see Warnings and Precautions (5.4)].
- Glomerulonephritis may occur. Symptoms include swelling of the face or ankles, dark colored urine or blood in the urine, or a decrease in urine production. Advise patients to report signs or symptoms of glomerulonephritis to their physician immediately [see Warnings and Precautions (5.5)].
- There may be an increased risk of Myelodysplastic Syndrome and/or Acute Myeloid Leukemia in patients with congenital neutropenia who receive filgrastim products and in patients with breast and lung cancer who receive filgrastim products in conjunction with chemotherapy and/or radiation therapy. Symptoms of MDS and AML may include tiredness, fever, and easy bruising or bleeding. Advise patients to report to their physician signs and symptoms of MDS/AML [see Warnings and Precautions (5.8)].
- Cutaneous vasculitis may occur, which may be signaled by purpura or erythema. Advise patients to report signs or symptoms of vasculitis to their physician immediately [see Warnings and Precautions (5.11)].
- Aortitis may occur. Symptoms may include fever, abdominal pain, malaise, back pain, and increased inflammatory markers. Advise patients to report signs and symptoms of aortitis to their physician immediately [see Warnings and Precautions (5.15)].

Advise patients acutely exposed to myelosuppressive doses of radiation (Hematopoietic Syndrome of Acute Radiation Syndrome) that efficacy studies of filgrastim products for this indication could not be conducted in humans for ethical and feasibility reasons and that, therefore, approval of this use was based on efficacy studies conducted in animals [see Clinical Studies (14.6)].

Instruct patients who self-administer NYPOZI using the prefilled syringes of the:

- Importance of following the applicable Instructions for Use.
- Dangers of reusing needles or syringes.
- Importance of following local requirements for proper disposal of used syringes and needles.
- Importance of informing the healthcare provider if difficulty occurs when measuring or administering partial contents of the NYPOZI prefilled syringe.

NYPOZI™ (filgrastim-txid)

NYPOZI is a trademark of Tanvex BioPharma USA, Inc.
Manufactured by:
Tanvex BioPharma USA, Inc,
10394 Pacific Center Court
San Diego, CA 92121
US License No. 2259

Patient Information
NYPOZI™ (ni-poz-ee)
(filgrastim-txid)
injection

What is NYPOZI?
NYPOZI is a man-made form of granulocyte colony-stimulating factor (G-CSF). G-CSF is a substance produced by the body. It stimulates the growth of neutrophils, a type of white blood cell important in the body's fight against infection.
Acute Radiation Syndrome: The effectiveness of filgrastim for this use was only studied in animals, because it could not be studied in people.

Do not take NYPOZI if you have had a serious allergic reaction to human G-CSFs such as filgrastim products or pegfilgrastim products.

Before you take NYPOZI, tell your healthcare provider about all of your medical conditions, including if you:

- have a sickle cell disorder.
- have kidney problems.
- are receiving radiation therapy.
- are pregnant or plan to become pregnant. It is not known if NYPOZI will harm your unborn baby.
- are breastfeeding or plan to breastfeed. It is not known if NYPOZI passes into your breast milk.

Tell your healthcare provider about all the medicines you take, including prescription and over-the-counter medicines, vitamins, and herbal supplements.

How will I receive NYPOZI?

- NYPOZI injections can be given by a healthcare provider by intravenous (IV) infusion or under your skin (subcutaneous injection). Your healthcare provider may decide subcutaneous injections can be given at home by you or your caregiver. If NYPOZI is given at home, see the detailed "Instructions for Use" that comes with your NYPOZI for information on how to prepare and inject a dose of NYPOZI.
- You and your caregiver should be shown how to prepare and inject NYPOZI before you use it, by your healthcare provider.
- Your healthcare provider will tell you how much NYPOZI to inject and when to inject it. Do not change your dose or stop NYPOZI unless your healthcare provider tells you to.
- You should not inject a dose of NYPOZI less than 0.3 mL (180 mcg) from a NYPOZI prefilled syringe. A dose less than 0.3 mL cannot be accurately measured using the NYPOZI prefilled syringe.
- If you are receiving NYPOZI because you are also receiving chemotherapy, your dose of NYPOZI should be injected at least 24 hours before or 24 hours after your dose of chemotherapy. Your healthcare provider will do blood tests to monitor your white blood cell counts, and if necessary, adjust your NYPOZI dose.
- If you are receiving NYPOZI because you have been suddenly (acutely) exposed to an amount of radiation that can affect your bone marrow (Acute Radiation Syndrome), you will need to have blood tests about every 3 days during treatment with NYPOZI to check your white blood cell count.
- If you miss a dose of NYPOZI, talk to your healthcare provider about when you should give your next dose.

What are the possible side effects of NYPOZI?
NYPOZI may cause serious side effects, including:

- Spleen rupture. Your spleen may become enlarged and can rupture. A ruptured spleen can cause death. Call your healthcare provider right away if you have pain in the left upper stomach (abdomen) area or your left shoulder.
- A serious lung problem called acute respiratory distress syndrome (ARDS). Call your healthcare provider or get emergency medical help right away if you have shortness of breath with or without a fever, trouble breathing, or a fast rate of breathing.
- Serious allergic reactions. NYPOZI can cause serious allergic reactions. These reactions can cause a rash over your whole body, shortness of breath, wheezing, dizziness, swelling around your mouth or eyes, fast heart rate, and sweating. If you have any of these symptoms, stop using NYPOZI and call your healthcare provider or get emergency medical help right away.
- Sickle cell crises. You may have a serious sickle cell crisis, which could lead to death, if you have a sickle cell disorder and receive NYPOZI. Call your healthcare provider right away if you have symptoms of sickle cell crisis such as pain or difficulty breathing.
- Kidney injury (glomerulonephritis). NYPOZI can cause kidney injury. Call your healthcare provider right away if you develop any of the following symptoms:
  - swelling of your face or ankles
  - blood in your urine or dark colored urine
  - you urinate less than usual
- Capillary leak syndrome. NYPOZI can cause fluid to leak from blood vessels into your body's tissues. This condition is called "Capillary Leak Syndrome" (CLS). CLS can quickly cause you to have symptoms that may become life-threatening. Get emergency medical help right away if you develop any of the following symptoms:
  - swelling or puffiness and are urinating less than usual
  - trouble breathing
  - swelling of your stomach-area (abdomen) and feeling of fullness
  - dizziness or feeling faint
  - a general feeling of tiredness
- Myelodysplastic syndrome (MDS) and acute myeloid leukemia (AML).
  - NYPOZI may increase the risk of developing a precancerous condition called MDS or a type of blood cancer called AML in people who were born with low white blood cell counts (congenital neutropenia).
  - If you have breast cancer or lung cancer, when NYPOZI is used with chemotherapy and radiation therapy or with radiation therapy only, you may have an increased risk of developing MDS or AML.
  - Symptoms of MDS and AML may include tiredness, fever, and easy bruising or bleeding.
  - Call your healthcare provider if you develop any of these symptoms during treatment with NYPOZI.
- Decreased platelet count (thrombocytopenia). Your healthcare provider will check your blood during treatment with NYPOZI. Tell your healthcare provider if you have unusual bleeding or bruising during treatment with NYPOZI. This could be a sign of decreased platelet counts, which may reduce the ability of your blood to clot.
- Increased white blood cell count (leukocytosis). Your healthcare provider will check your blood during treatment with NYPOZI.
- Inflammation of your blood vessels (cutaneous vasculitis). Tell your healthcare provider right away if you develop purple spots or redness of your skin.
- Inflammation of the aorta (aortitis). Inflammation of the aorta (the large blood vessel which transports blood from the heart to the body) has been reported in patients who received filgrastim products. Symptoms may include fever, abdominal pain, feeling tired, and back pain. Call your healthcare provider if you experience these symptoms.
  The most common side effects experienced in patients receiving NYPOZI include:
  - Patients with cancer receiving chemotherapy: fever, pain, rash, cough, and shortness of breath
  - Patients with acute myeloid leukemia receiving chemotherapy: pain, nose bleed, and rash
  - Patients with cancer receiving chemotherapy followed by bone marrow transplant: rash
  - Patients who are having their own blood cells collected: bone pain, fever, and headache
  - Patients with severe chronic neutropenia: pain, decreased red blood cells, nose bleed, diarrhea, reduced sensation, and hair loss

These are not all the possible side effects of NYPOZI. Call your healthcare provider for medical advice about side effects. You may report side effects to FDA at 1-800-FDA-1088.

How should I store NYPOZI?

- Store NYPOZI in the refrigerator between 36°F to 46°F (2°C to 8°C).
- Do not freeze.
- Keep NYPOZI in the original carton to protect it from light or physical damage. Do not leave NYPOZI in direct sunlight.
- Do not shake NYPOZI.
- Take NYPOZI out of the refrigerator 30 minutes before use and allow it to reach room temperature before preparing an injection.
- If not used right away, the prefilled syringe may be kept at room temperature between 68°F to 77°F (20°C to 25°C) for up to 24 hours. Throw away (dispose of) any NYPOZI that has been left at room temperature for more than 24 hours.
- After you inject your dose, throw away (dispose of) any unused NYPOZI left in the prefilled syringe. Do not save unused NYPOZI in the prefilled syringe for later use.

Keep NYPOZI and all medicines out of the reach of children.

General information about the safe and effective use of NYPOZI:
Medicines are sometimes prescribed for purposes other than those listed in a Patient Information leaflet. Do not use NYPOZI for a condition for which it was not prescribed. Do not give NYPOZI to other people, even if they have the same symptoms that you have. It may harm them. You can ask your pharmacist or healthcare provider for information about NYPOZI that is written for health professionals.

What are the ingredients in NYPOZI?
Active ingredient: filgrastim-txid
Inactive ingredients: glacial acetic acid, polysorbate 80, sodium acetate, sorbitol, and water for injection
tanvex
NYPOZI™
(filgrastim-txid) Injection
Manufactured by: Tanvex BioPharma USA, Inc., San Diego, CA 92121
Product of USA
US License No. 2259

This Patient Information has been approved by the U.S. Food and Drug Administration.

Issued: June 2024

Instructions for Use NYPOZI™ (ni-poz-ee) (filgrastim-txid) injection Single-Dose Prefilled Syringe

Guide to Parts

Important: The needle is covered by the gray needle cap before use.

Important

Read the Patient Information for important information you need to know about NYPOZI before using these Instructions for Use.

Before you use a NYPOZI prefilled syringe, read this important information.

Storing your NYPOZI prefilled syringe

- Store the NYPOZI prefilled syringe in the refrigerator between 36°F to 46°F (2°C to 8°C).
- Do not freeze NYPOZI prefilled syringes.
- Keep the prefilled syringe in the original carton to protect it from light or physical damage.
- Take the prefilled syringe out of the refrigerator 30 minutes before use and allow it to reach room temperature before preparing an injection.
- Throw away (dispose of) any prefilled syringe that has been left at room temperature for longer than 24 hours.
- After you inject your dose, throw away (dispose of) any unused NYPOZI left in the prefilled syringe. Do not save unused NYPOZI in the prefilled syringe for later use.
- Keep the NYPOZI prefilled syringe out of the reach of children.

Using your prefilled syringe

- It is important that you do not try to give the injection unless you or your caregiver has received training from your healthcare provider.
- Make sure the name NYPOZI appears on the carton and prefilled syringe label.
- Do not inject a dose of NYPOZI less than 0.3 mL (180 mcg) from a NYPOZI prefilled syringe. A dose less than 0.3 mL cannot be accurately measured using the NYPOZI prefilled syringe.
- Do not use a prefilled syringe after the expiration date on the label.
- Do not shake the prefilled syringe.
- Do not remove the gray needle cap from the prefilled syringe until you are ready to inject.
- Do not use the prefilled syringe if the carton is open or damaged.
- Do not use a prefilled syringe if it has been dropped on a hard surface. The prefilled syringe may be broken even if you cannot see the break. Use a new prefilled syringe.
- The prefilled syringe has a needle guard that will be activated to cover the needle after the injection is given. The needle guard will help prevent needle stick injuries to anyone who handles the prefilled syringe.
- Avoid touching the syringe needle guard wings before use. Touching them may cause the syringe needle guard to be activated too early. Use another prefilled syringe that has not been activated and is ready to use.

Call your healthcare provider if you have any questions.

Step 1: Prepare

A Remove the prefilled syringe carton from the refrigerator.

Put the original carton with any unused prefilled syringes back in the refrigerator.

Remove the syringe blister pack from the carton. On a clean, well-lit, flat surface, place the syringe blister pack at room temperature for 30 minutes before you give an injection.

- Do not use the prefilled syringe if the carton is damaged.
- Do not try to warm the prefilled syringe by using a heat source such as hot water or microwave.
- Keep the prefilled syringe in the blister pack until you are ready to use it.
- Do not leave the prefilled syringe in direct sunlight.
- Do not shake the prefilled syringe.

Open the blister pack by peeling away the cover. Grab the transparent needle guard to remove the prefilled syringe from the blister pack.

For safety reasons:

- Do not grab the plunger rod.
- Do not grab the gray needle cap.

B Inspect the medicine and prefilled syringe.

Turn the prefilled syringe so you can see through the viewing window and dose markings. Make sure the medicine in the prefilled syringe is clear and colorless to slightly yellowish.

Check to make sure that the plastic transparent needle guard is covering the barrel of the glass syringe. If the transparent needle guard is covering the gray needle cap (shown below), the needle guard has already been activated. Do not use the prefilled syringe if the needle guard has been activated.

Syringe with Activated Needle Guard

- Do not use the prefilled syringe if:
  - The medicine is cloudy or discolored or contains flakes or particles.
  - Any part appears cracked or broken.
  - The prefilled syringe has been dropped.
  - The gray needle cap is missing or not securely attached.
  - The expiration date printed on the label has passed.
- In all cases, use a new prefilled syringe and call your healthcare provider.

C Gather all materials needed for injection.

Wash your hands thoroughly with soap and water.

On a clean, well-lit work surface, place the:

- Prefilled syringe, and the following items, that are not included in the NYPOZI carton
- Alcohol wipe
- Cotton ball or gauze pad
- Adhesive bandage
- Sharps disposal container or other appropriate disposal container

Step 2: Get ready

D Prepare and clean your injection site

You can use:

- Thigh
- Stomach area (abdomen), except for a 2-inch area right around your navel (belly button)
- Upper outer area of your buttocks (only if someone else is giving you the injection)
- Outer area of upper arm (only if someone else is giving you the injection)

Clean your injection site with an alcohol wipe.

- Let your skin dry.
- Do not touch this cleansed area again before injecting.

If you want to use the same injection site, make sure it is not the same spot on the injection site area you used for a previous injection.

- Do not inject into areas where the skin is tender, bruised, red, scaly or hard. Avoid injecting into areas with scars or stretch marks.

E Hold the prefilled syringe by the syringe barrel (the clear plastic needle guard) with the needle pointing up. Carefully pull the gray needle cap straight off and away from your body.

- Do not remove the gray needle cap from the prefilled syringe until you are ready to inject.
- Do not twist or bend the gray needle cap.
- Do not hold the prefilled syringe by the plunger rod.
- Do not put the gray needle cap back onto the prefilled syringe.

Important: Throw away the gray needle cap into the sharps or other appropriate disposal container.

F Check your prescription before you inject your dose

Your healthcare provider has prescribed either a "full" syringe dose or a "partial" syringe dose of NYPOZI.

- If you are prescribed a full dose, you will inject all of the medicine from your prefilled syringe. For a full dose, go directly to Step 3: Subcutaneous (under the skin) injection.
- If you are prescribed a partial dose of NYPOZI, start with Step G below.

G Check the syringe for an air bubble. Point the needle up and gently tap the syringe with your fingers until the air bubble rises to the top of the syringe.

H Hold the syringe as shown below and press slowly on the plunger to push out the excess medicine until the top edge of the conical base of the plunger stopper lines up with the syringe marking for your prescribed dose. As you push the plunger rod up, air and extra medication is removed. Check to make sure the plunger lines up with the syringe markings for your prescribed dose. If you remove too much medicine, get a new prefilled syringe and start again at Step 1.

- See the figure below (Step 2) for an example of a dose of 0.4 mL. Your dose may be different than the example shown.
- Call your healthcare provider if you have problems measuring your prescribed dose.

Step 3: Subcutaneous (under the skin) injection

I With one hand gently pinch the skin at the injection site to create a firm surface.

Important: Keep the skin pinched while injecting.

J Hold the pinch. With your other hand insert the needle into the skin at a 45 to 90 degree angle as shown.

K Using slow and constant pressure, slowly press down on the plunger rod as far as it will go so that the plunger head is completely between the needle guard wings.

- Do not pull back the plunger rod while the needle is inserted.

When done, keep the plunger fully pressed down while you carefully pull the needle straight out from the injection site.

Important: When you remove the syringe, if it looks like the medicine is still in the syringe barrel, this means you have not received a full dose. Call your healthcare provider right away.

Step 4: Finish

L Before you finish!

Slowly release the plunger and allow the needle guard to automatically cover the exposed needle.

Keep your hands away from the needle at all times.

M Discard (throw away) your used prefilled syringe.

- Put the used prefilled syringe in a FDA-cleared sharps or other appropriate disposal container right away after use. Do not throw away (dispose of) your NYPOZI prefilled syringe in your household trash.
- If you do not have a FDA-cleared sharps disposal container, you may use a household container that is:
  - made of a heavy-duty plastic,
  - can be closed with a tight-fitting, puncture-resistant lid, without sharps being able to come out,
  - upright and stable during use,
  - leak-resistant, and
  - properly labeled to warn of hazardous waste inside the container.
- When your sharps disposal container is almost full, you will need to follow your community guidelines for the right way to dispose of your sharps disposal container. There may be state or local laws about how you should throw away used needles, syringes, and prefilled syringes. For more information about safe sharps disposal, and for specific information about sharps disposal in the state that you live in, go to the FDA's website at: http://www.fda.gov/safesharpsdisposal.
- Do not reuse the prefilled syringe.
- Do not recycle the prefilled syringe or sharps disposal container or throw them into household trash.

Important: Always keep the sharps disposal container out of the reach of children.

N Examine the injection site.

If there is blood, press a cotton ball or gauze pad on your injection site. Do not rub the injection site. Apply an adhesive bandage if needed.

tanvex
NYPOZI™
(filgrastim-txid) Injection

Manufactured by:
Tanvex BioPharma USA, Inc., San Diego, CA 92121
Product of USA
US License No. 2259

This Instructions for Use has been approved by the U.S. Food and Drug Administration.
Issued: June 2024

PRINCIPAL DISPLAY PANEL - (1) 0.5 mL Syringe Carton

1 x 300 mcg/0.5 mL Single-Dose Prefilled Syringe with a Needle Guard

NDC 72374-101-01

Rx Only

NYPOZI™
(filgrastim-txid) injection

300 mcg/0.5 mL

A Recombinant Granulocyte Colony Stimulating Factor (rG-CSF) derived from E. Coli
For Subcutaneous Use or Intravenous Use Only

If required for intravenous administration, dilute in 5% Dextrose Injection
to a concentration of 15 mcg/mL. To protect from adsorption to plastic
materials, add Albumin (Human) to a final concentration of 2 mg/mL.

Single-Dose Prefilled Syringe. Discard Unused Portion.

tanvex

PRINCIPAL DISPLAY PANEL - (10) 0.5 mL Syringe Carton

10 x 300 mcg/0.5 mL Single-Dose Prefilled Syringes with a Needle Guard

NDC 72374-101-10

Rx Only

NYPOZI™
(filgrastim-txid) injection

300 mcg/0.5 mL

A Recombinant Granulocyte Colony Stimulating Factor (rG-CSF) derived from E. Coli
For Subcutaneous Use or Intravenous Use Only

If required for intravenous administration, dilute in 5% Dextrose Injection to a
concentration of 15 mcg/mL. To protect from adsorption to plastic materials,
add Albumin (Human) to a final concentration of 2 mg/mL.

Single-Dose Prefilled Syringe. Discard Unused Portion.

Manufactured by:
Tanvex BioPharma USA, Inc., San Diego, CA 92121 USA
U.S. License No. 2259

tanvex

PRINCIPAL DISPLAY PANEL - (1) 0.8 mL Syringe Carton

1 x 480 mcg/0.8 mL Single-Dose Prefilled Syringe with a Needle Guard

NDC 72374-102-01

Rx Only

NYPOZI™
(filgrastim-txid) injection

480 mcg/0.8 mL

A Recombinant Granulocyte Colony Stimulating Factor (rG-CSF) derived from E. Coli
For Subcutaneous Use or Intravenous Use Only

If required for intravenous administration, dilute in 5% Dextrose Injection
to a concentration of 15 mcg/mL. To protect from adsorption to plastic
materials, add Albumin (Human) to a final concentration of 2 mg/mL.

Single-Dose Prefilled Syringe. Discard Unused Portion.

tanvex

PRINCIPAL DISPLAY PANEL - (10) 0.8 mL Syringe Carton

10 x 480 mcg/0.8 mL Single-Dose Prefilled Syringes with a Needle Guard

NDC 72374-102-10

Rx Only

NYPOZI™
(filgrastim-txid) injection

480 mcg/0.8 mL

A Recombinant Granulocyte Colony Stimulating Factor (rG-CSF) derived from E. Coli
For Subcutaneous Use or Intravenous Use Only

If required for intravenous administration, dilute in 5% Dextrose Injection to a
concentration of 15 mcg/mL. To protect from adsorption to plastic materials,
add Albumin (Human) to a final concentration of 2 mg/mL.

Single-Dose Prefilled Syringe. Discard Unused Portion.

Manufactured by:
Tanvex BioPharma USA, Inc., San Diego, CA 92121 USA
U.S. License No. 2259

tanvex